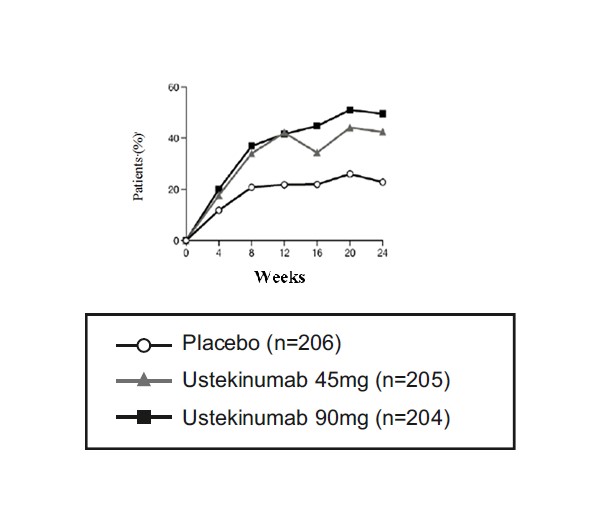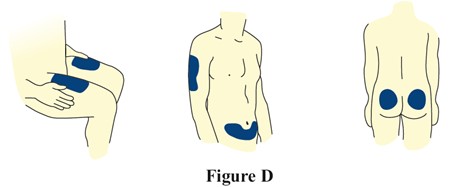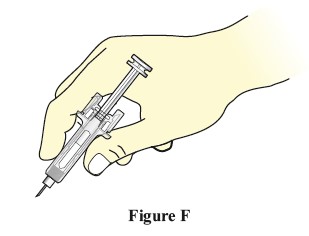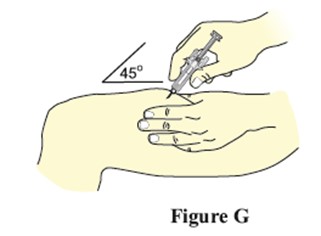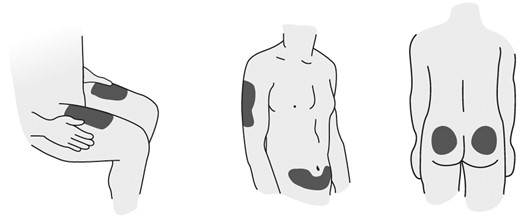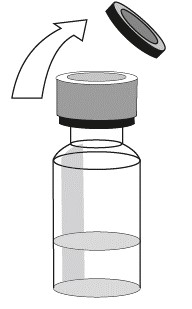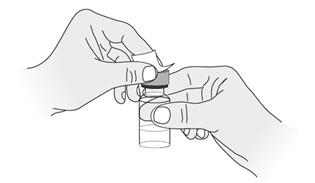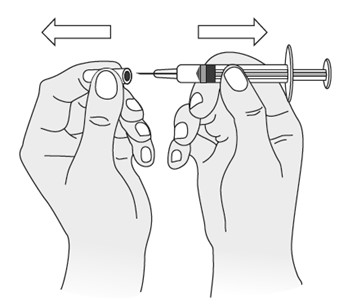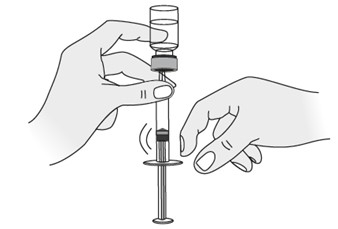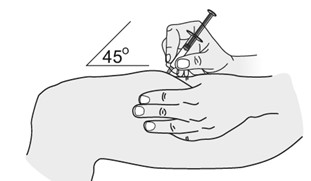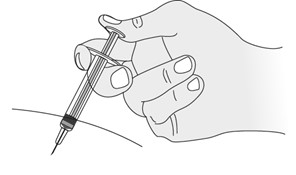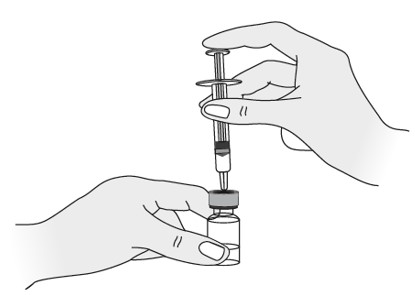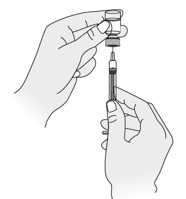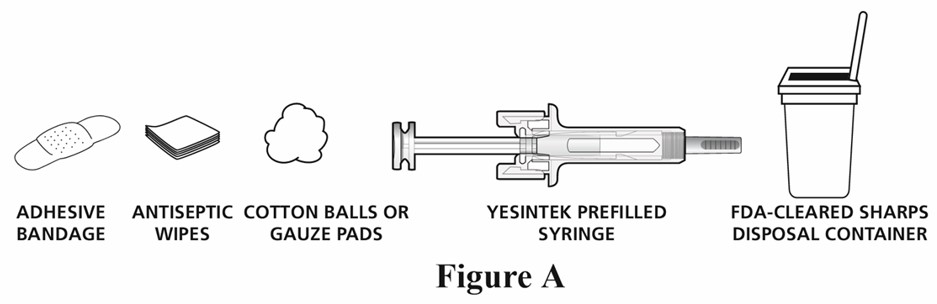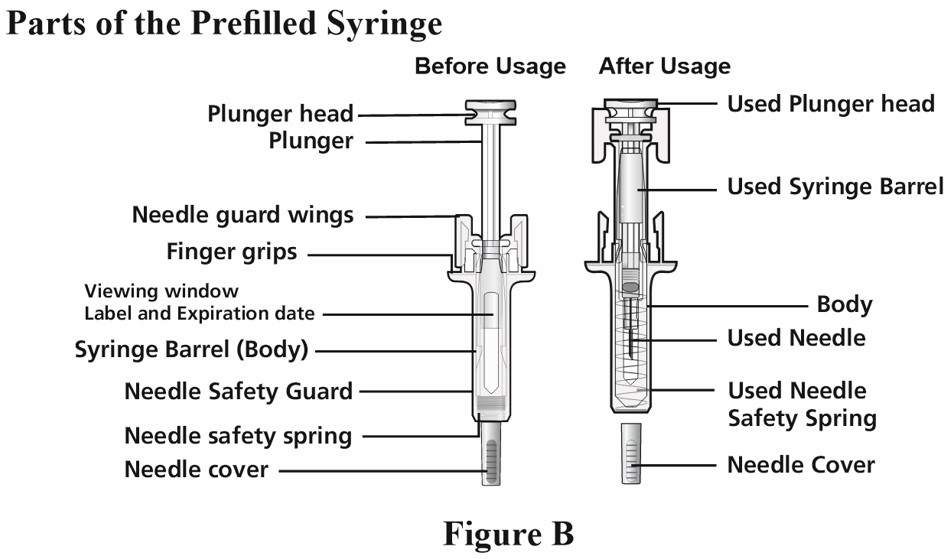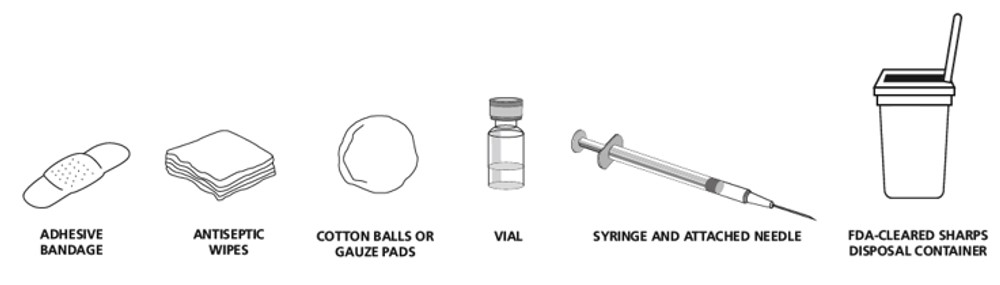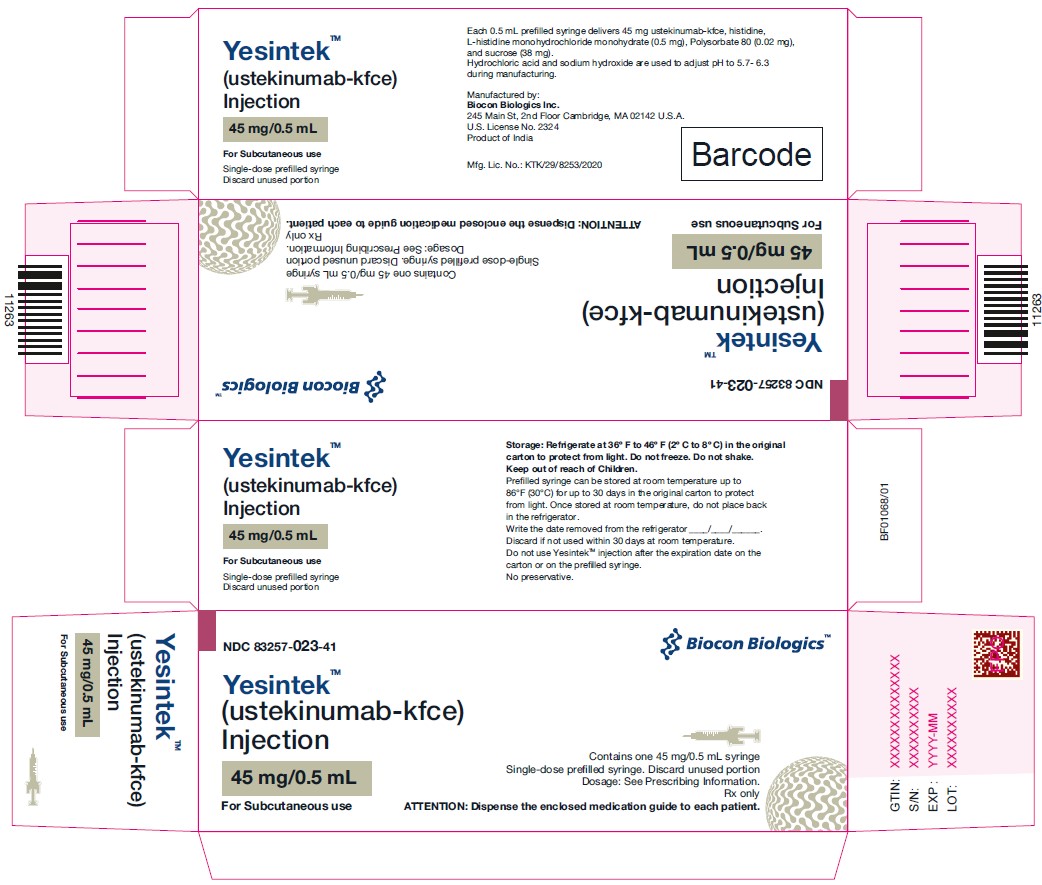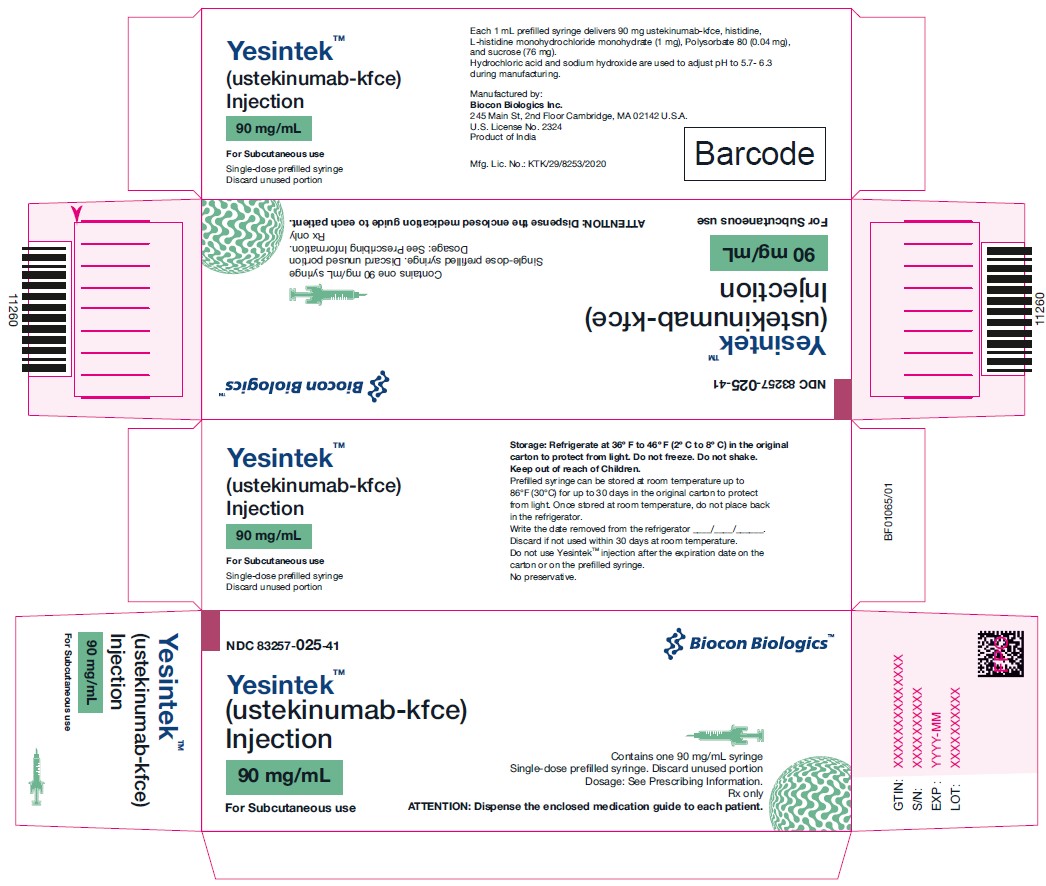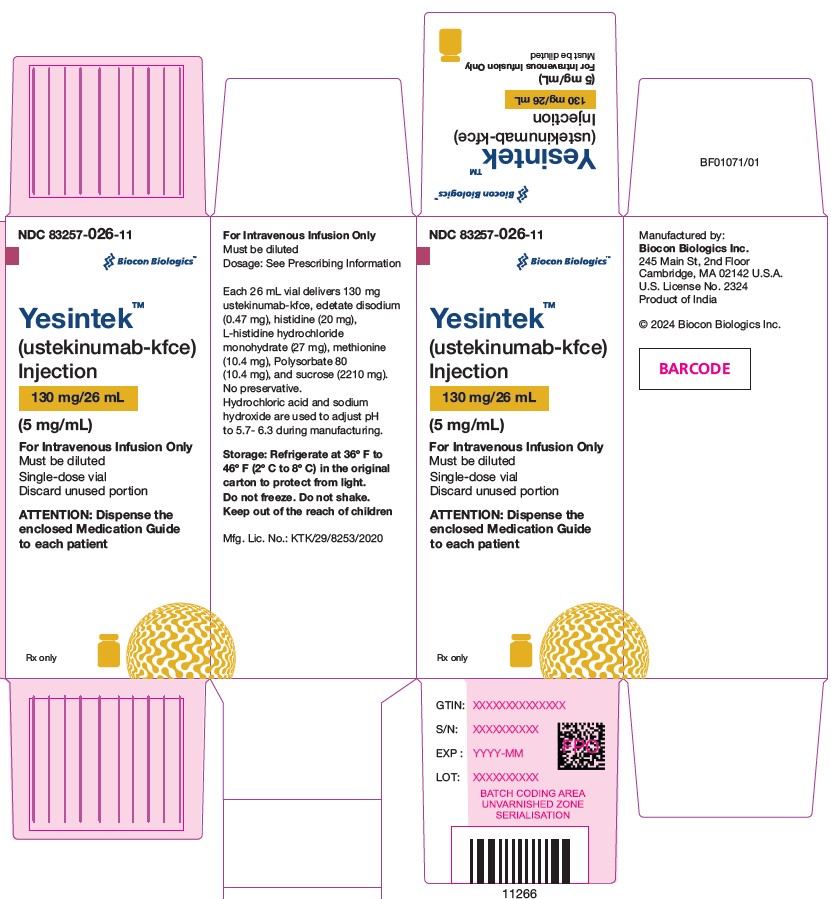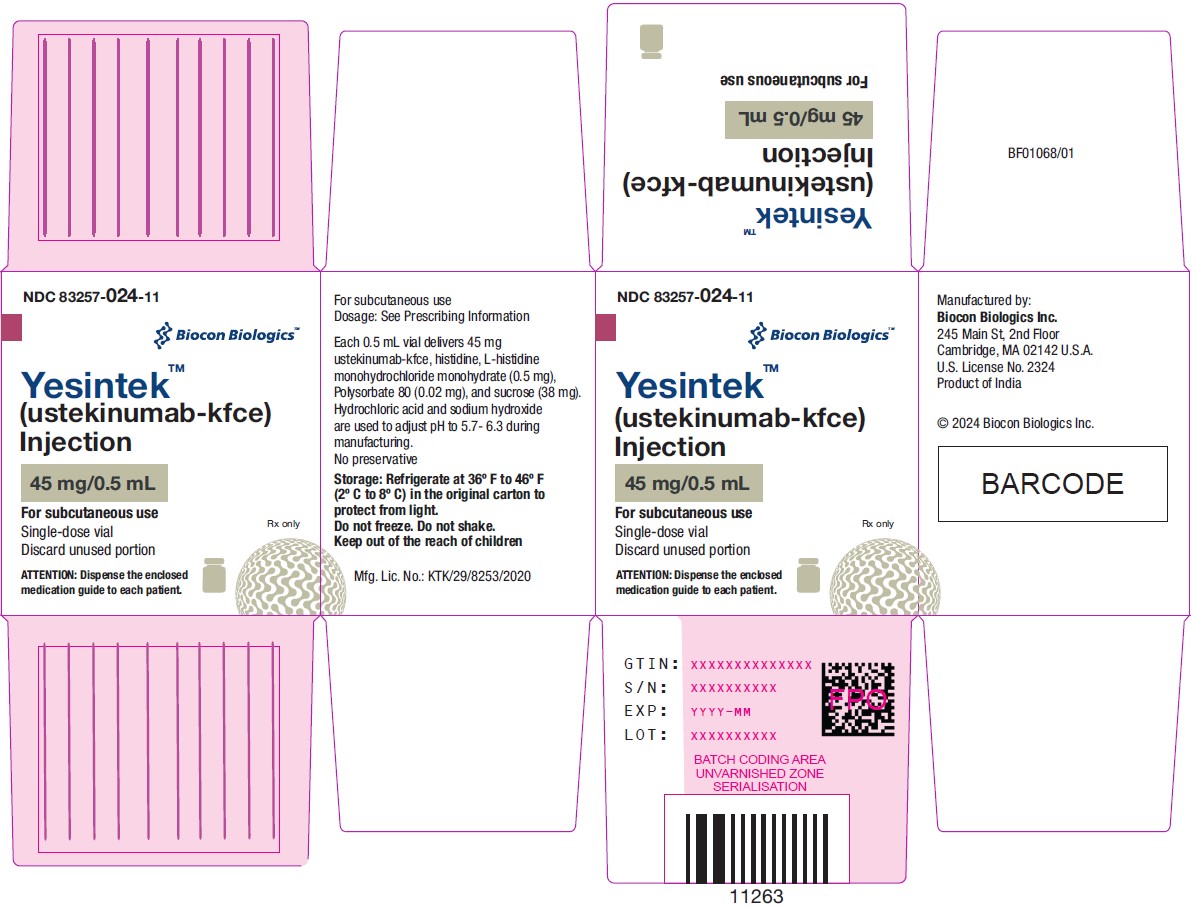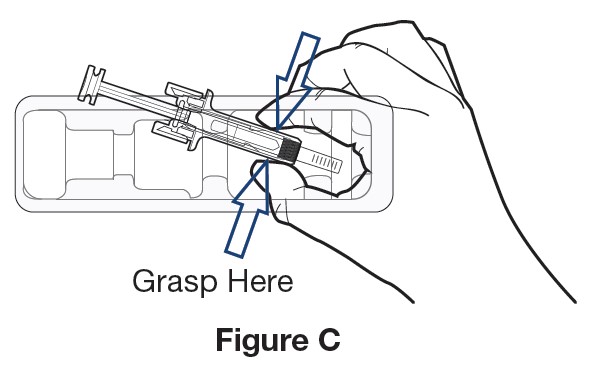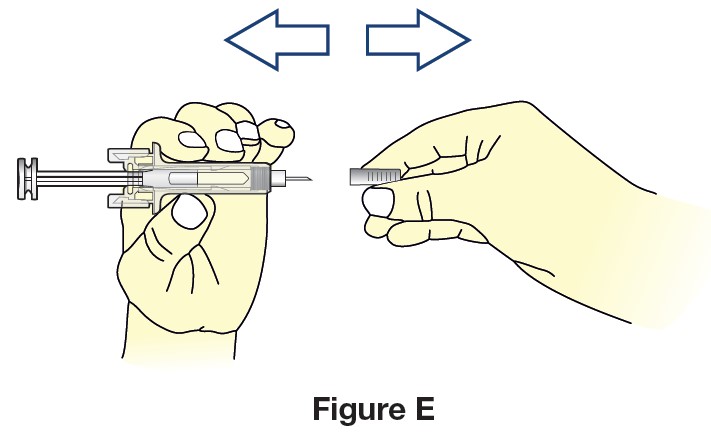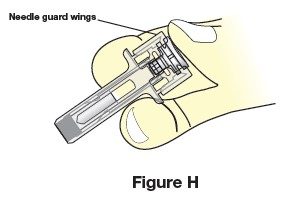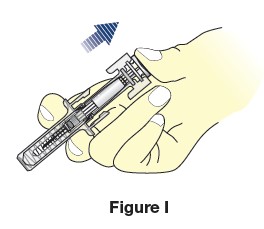 DRUG LABEL: YESINTEK
NDC: 83257-024 | Form: INJECTION, SOLUTION
Manufacturer: Biocon Biologics Inc.
Category: prescription | Type: HUMAN PRESCRIPTION DRUG LABEL
Date: 20251209

ACTIVE INGREDIENTS: ustekinumab 45 mg/0.5 mL
INACTIVE INGREDIENTS: sucrose 38 mg/0.5 mL; polysorbate 80 0.02 mg/0.5 mL; HISTIDINE 0.5 mg/0.5 mL; HISTIDINE MONOHYDROCHLORIDE MONOHYDRATE; water

HIGHLIGHTS OF PRESCRIBING INFORMATION

These highlights do not include all the information needed to use YESINTEK safely and effectively. See full prescribing information for YESINTEK.
YESINTEKTM (ustekinumab-kfce) injection, for subcutaneous or intravenous use
Initial U.S. Approval: 2024
YESINTEKTM (ustekinumab-kfce) is biosimilar* to STELARA® (ustekinumab).

RECENT MAJOR CHANGES

Warnings and Precautions

- Serious Hypersensitivity Reactions (5.5) 01/2026

1 INDICATIONS AND USAGE

YESINTEK is a human interleukin-12 and -23 antagonist indicated for the treatment of:

Adult patients with:

- moderate to severe plaque psoriasis (PsO) who are candidates for phototherapy or systemic therapy. (1.1)
- active psoriatic arthritis (PsA). (1.2)
- moderately to severely active Crohn’s disease (CD). (1.3)
- moderately to severely active ulcerative colitis. (1.4)

Pediatric patients 6 years and older with:

- moderate to severe plaque psoriasis (PsO), who are candidates for phototherapy or systemic therapy. (1.1)
- active psoriatic arthritis (PsA). (1.2)

2 DOSAGE AND ADMINISTRATION

Adult Patients with Plaque Psoriasis Subcutaneous Recommended Dosage (2.1):

Weight Range (kilograms) | Dosage
less than or equal to 100 kg | 45 mg administered subcutaneously initially and 4 weeks later, followed by 45 mg administered subcutaneously every 12 weeks
greater than 100 kg | 90 mg administered subcutaneously initially and 4 weeks later, followed by 90 mg administered subcutaneously every 12 weeks

Pediatric Patients 6 Years of Age and Older with Plaque Psoriasis Subcutaneous Recommended Dosage (2.1): Weight-based dosing is recommended at the initial dose, 4 weeks later, then every 12 weeks thereafter.

Weight Range (kilograms) | Dose
less than 60 kg | 0.75 mg/kg
60 kg to 100 kg | 45 mg
greater than 100 kg | 90 mg

Psoriatic Arthritis Adult Subcutaneous Recommended Dosage (2.2):

- The recommended dosage is 45 mg administered subcutaneously initially and 4 weeks later, followed by 45 mg administered subcutaneously every 12 weeks.
- For patients with co-existent moderate-to-severe plaque psoriasis weighing greater than 100 kg, the recommended dosage is 90 mg administered subcutaneously initially and 4 weeks later, followed by 90 mg administered subcutaneously every 12 weeks.

Psoriatic Arthritis Pediatric (6 years of Age and Older Subcutaneous Recommended Dosage (2.2): Weight-based dosing is recommended at the initial dose, 4 weeks later, then every 12 weeks thereafter.

Weight Range (kilograms) | Dose
less than 60 kg | 0.75 mg/kg
60 kg or more | 45 mg
greater than 100 kg with co-existent moderate-to-severe plaque psoriasis | 90 mg

Crohn's Disease and Ulcerative Colitis Initial Adult Intravenous Recommended Dose (2.3):

A single intravenous infusion using weight-based dosing:

Weight Range (kilograms) | Recommended Dose
up to 55 kg | 260 mg (2 vials)
greater than 55 kg to 85 kg | 390 mg (3 vials)
greater than 85 kg | 520 mg (4 vials)

Crohn's Disease and Ulcerative Colitis Maintenance Adult Subcutaneous Recommended Dosage (2.3):

A subcutaneous 90 mg dose 8 weeks after the initial intravenous dose, then every 8 weeks thereafter.

3 DOSAGE FORMS AND STRENGTHS

Subcutaneous Injection (3)

- Injection: 45 mg/0.5 mL or 90 mg/mL solution in a single-dose prefilled syringe
- Injection: 45 mg/0.5 mL solution in a single-dose vial

Intravenous Infusion (3)

- Injection: 130 mg/26 mL (5 mg/mL) solution in a single-dose vial (3)

4 CONTRAINDICATIONS

Clinically significant hypersensitivity to ustekinumab products or to any of the excipients in YESINTEK. (4)

5 WARNINGS AND PRECAUTIONS

- Infections: Serious infections have occurred. Avoid starting YESINTEK during any clinically important active infection. If a serious infection or clinically significant infection develops, discontinue YESINTEK until the infection resolves. (5.1)
- Theoretical Risk for Particular Infections: Serious infections from mycobacteria, salmonella, and Bacillus Calmette-Guerin (BCG) vaccinations have been reported in patients genetically deficient in IL-12/IL-23. Consider diagnostic tests for these infections as dictated by clinical circumstances. (5.2)
- Tuberculosis (TB): Evaluate patients for TB prior to initiating treatment with YESINTEK. Initiate treatment of latent TB before administering YESINTEK. (5.3)
- Malignancies: Ustekinumab products may increase risk of malignancy. The safety of ustekinumab products in patients with a history of or a known malignancy has not been evaluated. (5.4)
- Serious Hypersensitivity Reactions: If a severe or other clinically significant hypersensitivity reaction occurs, discontinue YESINTEK immediately and initiate appropriate medical treatment. (5.5)
- Posterior Reversible Encephalopathy Syndrome (PRES): If PRES is suspected, treat promptly, and discontinue YESINTEK. (5.6)
- Immunizations: Avoid use of live vaccines in patients during treatment with YESINTEK. (5.7)
- Noninfectious Pneumonia: Cases of interstitial pneumonia, eosinophilic pneumonia, and cryptogenic organizing pneumonia have been reported during post-approval use of ustekinumab products. If diagnosis is confirmed, discontinue YESINTEK and institute appropriate treatment. (5.8)

6 ADVERSE REACTIONS

Most common adverse reactions are:

- Psoriasis and Psoriatic Arthritis (≥3%): nasopharyngitis, upper respiratory tract infection, headache, and fatigue. (6.1)
- Crohn’s Disease, induction (≥3%): vomiting. (6.1)
- Crohn’s Disease, maintenance (≥3%): nasopharyngitis, injection site erythema, vulvovaginal candidiasis/mycotic infection, bronchitis, pruritus, urinary tract infection, and sinusitis. (6.1)
- Ulcerative colitis, induction (≥3%): nasopharyngitis (6.1)
- Ulcerative colitis, maintenance (≥3%): nasopharyngitis, headache, abdominal pain, influenza, fever, diarrhea, sinusitis, fatigue, and nausea (6.1)

To report SUSPECTED ADVERSE REACTIONS, contact Biocon Biologics at 1-833-986-1468 or FDA at 1-800-FDA-1088 or www.fda.gov/medwatch.

*Biosimilar means that the biological product is approved based on data demonstrating that it is highly similar to an FDA-approved biological product, known as a reference product, and that there are no clinically meaningful differences between the biosimilar product and the reference product. Biosimilarity of YESINTEK has been demonstrated for the condition(s) of use (e.g., indication(s), dosing regimen(s)), strength(s), dosage form(s), and route(s) of administration described in its Full Prescribing Information.

FULL PRESCRIBING INFORMATION

1 INDICATIONS AND USAGE

1.1 Plaque Psoriasis (PsO)

YESINTEK is indicated for the treatment of adults and pediatric patients 6 years of age and older with moderate to severe plaque psoriasis who are candidates for phototherapy or systemic therapy.

1.2 Psoriatic Arthritis (PsA)

YESINTEK is indicated for the treatment of adults and pediatric patients 6 years of age and older with active psoriatic arthritis.

1.3 Crohn's Disease (CD)

YESINTEK is indicated for the treatment of adult patients with moderately to severely active Crohn's disease.

1.4 Ulcerative Colitis

YESINTEK is indicated for the treatment of adult patients with moderately to severely active ulcerative colitis.

2 DOSAGE AND ADMINISTRATION

2.1 Recommended Dosage in Plaque Psoriasis

Subcutaneous Adult Dosage Regimen

- For patients weighing 100 kg or less, the recommended dosage is 45 mg initially and 4 weeks later, followed by 45 mg every 12 weeks.
- For patients weighing more than 100 kg, the recommended dosage is 90 mg initially and 4 weeks later, followed by 90 mg every 12 weeks.

In subjects weighing more than 100 kg, 45 mg was also shown to be efficacious. However, 90 mg resulted in greater efficacy in these subjects [see Clinical Studies (14)].

Subcutaneous Pediatric Dosage Regimen

Administer YESINTEK subcutaneously at Weeks 0 and 4, then every 12 weeks thereafter.

The recommended dose of YESINTEK for pediatric patients 6 years of age and older with plaque psoriasis based on body weight is shown below (Table 1).

Table 1: Recommended Dose of YESINTEK for Subcutaneous Injection in Pediatric Patients 6 Years of Age and Older With Plaque Psoriasis

Body Weight of Patient at the Time of Dosing | Recommended Dose
less than 60 kg | 0.75 mg/kg
60 kg to 100 kg | 45 mg
more than 100 kg | 90 mg

For pediatric patients weighing less than 60 kg, the administration volume for the recommended dose (0.75 mg/kg) is shown in Table 2; withdraw the appropriate volume from the vial.

Table 2: Injection volumes of YESINTEK 45 mg/0.5 mL Vials for Pediatric Patients 6 Years of Age and Older With Plaque Psoriasis and Pediatric Patients 6 Years of Age and Older With Psoriatic Arthritis* Weighing Less Than 60 kg

Body Weight (kg) at the time of dosing | Dose (mg) | Volume of injection (mL)
15 | 11.3 | 0.12
16 | 12 | 0.13
17 | 12.8 | 0.14
18 | 13.5 | 0.15
19 | 14.3 | 0.16
20 | 15 | 0.17
21 | 15.8 | 0.17
22 | 16.5 | 0.18
23 | 17.3 | 0.19
24 | 18 | 0.2
25 | 18.8 | 0.21
26 | 19.5 | 0.22
27 | 20.3 | 0.22
28 | 21 | 0.23
29 | 21.8 | 0.24
30 | 22.5 | 0.25
31 | 23.3 | 0.26
32 | 24 | 0.27
33 | 24.8 | 0.27
34 | 25.5 | 0.28
35 | 26.3 | 0.29
36 | 27 | 0.3
37 | 27.8 | 0.31
38 | 28.5 | 0.32
39 | 29.3 | 0.32
40 | 30 | 0.33
41 | 30.8 | 0.34
42 | 31.5 | 0.35
43 | 32.3 | 0.36
44 | 33 | 0.37
45 | 33.8 | 0.37
46 | 34.5 | 0.38
47 | 35.3 | 0.39
48 | 36 | 0.4
49 | 36.8 | 0.41
50 | 37.5 | 0.42
51 | 38.3 | 0.42
52 | 39 | 0.43
53 | 39.8 | 0.44
54 | 40.5 | 0.45
55 | 41.3 | 0.46
56 | 42 | 0.46
57 | 42.8 | 0.47
58 | 43.5 | 0.48
59 | 44.3 | 0.49

* Refer to 2.2 Psoriatic Arthritis; Subcutaneous Pediatric Dosage Regimen.

2.2 Recommended Dosage in Psoriatic Arthritis

Subcutaneous Adult Dosage Regimen

- The recommended dosage is 45 mg initially and 4 weeks later, followed by 45 mg every 12 weeks.
- For patients with co-existent moderate-to-severe plaque psoriasis weighing more than 100 kg, the recommended dosage is 90 mg initially and 4 weeks later, followed by 90 mg every 12 weeks.

Subcutaneous Pediatric Dosage Regimen

Administer YESINTEK subcutaneously at Weeks 0 and 4, then every 12 weeks thereafter.

The recommended dose of YESINTEK for pediatric patients 6 years of age and older with psoriatic arthritis, based on body weight, is shown below (Table 3).

Table 3: Recommended Dose of YESINTEK for Subcutaneous Injection in Pediatric Patients 6 Years of Age and Older With Psoriatic Arthritis

Body Weight of Patient at the Time of Dosing | Recommended Dose
less than 60 kg [For pediatric patients weighing less than 60 kg, the administration volume for the recommended dose (0.75 mg/kg) is shown in Table 2; withdraw the appropriate volume from the vial.] | 0.75 mg/kg
60 kg or more | 45 mg
greater than 100 kg with co-existent moderate-to-severe plaque psoriasis | 90 mg

2.3 Recommended Dosage in Crohn's Disease and Ulcerative Colitis

Intravenous Induction Adult Dosage Regimen

A single intravenous infusion dose of YESINTEK using the weight-based dosage regimen specified in Table 4 [see Instructions for dilution of YESINTEK 130 mg vial for intravenous infusion (2.5)].

Table 4: Initial Intravenous Dosage of YESINTEK
Body Weight of Patient at the time of dosing | Dose | Number of 130 mg/26 mL (5 mg/mL) YESINTEK vials
55 kg or less | 260 mg | 2
more than 55 kg to 85 kg | 390 mg | 3
more than 85 kg | 520 mg | 4

Subcutaneous Maintenance Adult Dosage Regimen

The recommended maintenance dosage is a subcutaneous 90 mg dose administered 8 weeks after the initial intravenous dose, then every 8 weeks thereafter.

2.4 General Considerations for Administration

- YESINTEK is intended for use under the guidance and supervision of a healthcare provider. YESINTEK should only be administered to patients who will be closely monitored and have regular follow-up visits with a healthcare provider. The appropriate dose should be determined by a healthcare provider using the patient’s current weight at the time of dosing. In pediatric patients, it is recommended that YESINTEK be administered by a healthcare provider. If a healthcare provider determines that it is appropriate, a patient may self-inject or a caregiver may inject YESINTEK after proper training in subcutaneous injection technique. Instruct patients to follow the directions provided in the Instructions for Use [see Instructions for Use].
- It is recommended that each injection be administered at a different anatomic location (such as upper arms, gluteal regions, thighs, or any quadrant of abdomen) than the previous injection, and not into areas where the skin is tender, bruised, erythematous, or indurated. When using the vial, a 1 mL syringe with a 27 gauge, ½ inch needle is recommended.
- Prior to administration, visually inspect YESINTEK for particulate matter and discoloration. YESINTEK is a clear, colorless to pale yellow solution. Do not use YESINTEK if it is discolored or cloudy, or if other particulate matter is present. YESINTEK does not contain preservatives; therefore, discard any unused product remaining in the vial and/or syringe.

2.5 Preparation and Administration of YESINTEK 130 mg/26 mL (5 mg/mL) Vial for Intravenous Infusion (Crohn's Disease and Ulcerative Colitis)

YESINTEK solution for intravenous infusion must be diluted, prepared and infused by a healthcare professional using aseptic technique.

1. Calculate the dose and the number of YESINTEK vials needed based on patient weight (Table 4). Each 26 mL vial of YESINTEK contains 130 mg of ustekinumab-kfce.
2. Withdraw, and then discard a volume of the 0.9% Sodium Chloride Injection, USP from the 250 mL infusion bag equal to the volume of YESINTEK to be added (discard 26 mL sodium chloride for each vial of YESINTEK needed, for 2 vials- discard 52 mL, for 3 vials- discard 78 mL, 4 vials- discard 104 mL). Alternatively, a 250 mL infusion bag containing 0.45% Sodium Chloride Injection, USP may be used.
3. Withdraw 26 mL of YESINTEK from each vial needed and add it to the 250 mL infusion bag. The final volume in the infusion bag should be 250 mL. Gently mix.
4. Visually inspect the diluted solution before infusion. Do not use if visibly opaque particles, discoloration or foreign particles are observed.
5. Infuse the diluted solution over a period of at least one hour. Once diluted, the infusion should be completely administered within four hours of the dilution in the infusion bag.
6. Use only an infusion set with an in-line, sterile, non-pyrogenic, low protein-binding filter (pore size 0.2 micrometer).
7. Do not infuse YESINTEK concomitantly in the same intravenous line with other agents.
8. YESINTEK does not contain preservatives. Each vial is for a one-time use in only one patient. Discard any remaining solution. Dispose any unused medicinal product in accordance with local requirements.

Storage

If necessary, the diluted infusion solution may be kept at room temperature up to 25°C (77°F) for up to 4 hours. Storage time at room temperature begins once the diluted solution has been prepared. The infusion should be completed within 4 hours after the dilution in the infusion bag (cumulative time after preparation including the storage and the infusion period). Do not freeze. Discard any unused portion of the infusion solution.

3 DOSAGE FORMS AND STRENGTHS

YESINTEK (ustekinumab-kfce) is a clear and colorless to pale yellow solution.

Subcutaneous Injection

- Injection: 45 mg/0.5 mL or 90 mg/mL solution in a single-dose prefilled syringe
- Injection: 45 mg/0.5 mL solution in a single-dose vial

Intravenous Infusion

- Injection: 130 mg/26 mL (5 mg/mL) solution in a single-dose vial

4 CONTRAINDICATIONS

YESINTEK is contraindicated in patients with clinically significant hypersensitivity to ustekinumab products or to any of the excipients in YESINTEK [see Warnings and Precautions (5.5)].

5 WARNINGS AND PRECAUTIONS

5.1 Infections

Ustekinumab products may increase the risk of infections and reactivation of latent infections. Serious bacterial, mycobacterial, fungal, and viral infections were observed in patients receiving ustekinumab products [see Adverse Reactions (6.1, 6.3)].

Serious infections requiring hospitalization, or otherwise clinically significant infections, reported in clinical trials included the following:

- Plaque Psoriasis: diverticulitis, cellulitis, pneumonia, appendicitis, cholecystitis, sepsis, osteomyelitis, viral infections, gastroenteritis, and urinary tract infections.
- Psoriatic arthritis: cholecystitis.
- Crohn's disease: anal abscess, gastroenteritis, ophthalmic herpes zoster, pneumonia, and listeria meningitis.
- Ulcerative colitis: gastroenteritis, ophthalmic herpes zoster, pneumonia, and listeriosis.

Avoid initiating treatment with YESINTEK in patients with any clinically important active infection until the infection resolves or is adequately treated. Consider the risks and benefits of treatment prior to initiating use of YESINTEK in patients with a chronic infection or a history of recurrent infection.

Instruct patients to seek medical advice if signs or symptoms suggestive of an infection occur while on treatment with YESINTEK and discontinue YESINTEK for serious or clinically significant infections until the infection resolves or is adequately treated.

5.2 Theoretical Risk for Vulnerability to Particular Infections

Individuals genetically deficient in IL-12/IL-23 are particularly vulnerable to disseminated infections from mycobacteria (including nontuberculous, environmental mycobacteria), salmonella (including nontyphi strains), and Bacillus Calmette-Guerin (BCG) vaccinations. Serious infections and fatal outcomes have been reported in such patients.

It is not known whether patients with pharmacologic blockade of IL-12/IL-23 from treatment with ustekinumab products may be susceptible to these types of infections. Consider appropriate diagnostic testing, (e.g., tissue culture, stool culture, as dictated by clinical circumstances).

5.3 Pre-treatment Evaluation for Tuberculosis

Evaluate patients for tuberculosis infection prior to initiating treatment with YESINTEK.

Avoid administering YESINTEK to patients with active tuberculosis infection. Initiate treatment of latent tuberculosis prior to administering YESINTEK. Consider anti-tuberculosis therapy prior to initiation of YESINTEK in patients with a past history of latent or active tuberculosis in whom an adequate course of treatment cannot be confirmed. Closely monitor patients receiving YESINTEK for signs and symptoms of active tuberculosis during and after treatment.

5.4 Malignancies

Ustekinumab products are immunosuppressants and may increase the risk of malignancy. Malignancies were reported among subjects who received ustekinumab in clinical trials [see Adverse Reactions (6.1)]. In rodent models, inhibition of IL-12/IL-23p40 increased the risk of malignancy [see Nonclinical Toxicology (13)].

The safety of ustekinumab products has not been evaluated in patients who have a history of malignancy or who have a known malignancy.

There have been post-marketing reports of the rapid appearance of multiple cutaneous squamous cell carcinomas in patients receiving ustekinumab products who had pre-existing risk factors for developing non-melanoma skin cancer. Monitor all patients receiving YESINTEK for the appearance of non-melanoma skin cancer. Closely follow patients greater than 60 years of age, those with a medical history of prolonged immunosuppressant therapy and those with a history of PUVA treatment [see Adverse Reactions (6.1)].

5.5 Serious Hypersensitivity Reactions

Serious hypersensitivity reactions, including anaphylaxis and angioedema, have been reported with ustekinumab products in clinical trials and postmarketing. Some serious hypersensivitiy reactions have occurred during the first intravenous dose of ustekinumab products [see Adverse Reactions (6.1, 6.3)]. If a severe or clinically significant hypersensitivity reaction occurs, discontinue YESINTEK immediately and initiate appropriate medical treatment [see Contraindications (4)].

5.6 Posterior Reversible Encephalopathy Syndrome (PRES)

Two cases of posterior reversible encephalopathy syndrome (PRES), also known as Reversible Posterior Leukoencephalopathy Syndrome (RPLS), were reported in clinical trials. Cases have also been reported in postmarketing experience in patients with psoriasis, psoriatic arthritis, and Crohn's disease. Clinical presentation included headaches, seizures, confusion, visual disturbances, and imaging changes consistent with PRES a few days to several months after ustekinumab product initiation. A few cases reported latency of a year or longer. Patients recovered with supportive care following withdrawal of ustekinumab products.

Monitor all patients treated with YESINTEK for signs and symptoms of PRES. If PRES is suspected, promptly administer appropriate treatment and discontinue YESINTEK.

5.7 Immunizations

Prior to initiating therapy with YESINTEK, patients should receive all age-appropriate immunizations as recommended by current immunization guidelines. Patients being treated with YESINTEK should avoid receiving live vaccines. Avoid administering BCG vaccines during treatment with YESINTEK or for one year prior to initiating treatment or one year following discontinuation of treatment. Caution is advised when administering live vaccines to household contacts of patients receiving YESINTEK because of the potential risk for shedding from the household contact and transmission to patient.

Non-live vaccinations received during a course of YESINTEK may not elicit an immune response sufficient to prevent disease.

5.8 Noninfectious Pneumonia

Cases of interstitial pneumonia, eosinophilic pneumonia, and cryptogenic organizing pneumonia have been reported during post-approval use of ustekinumab products. Clinical presentations included cough, dyspnea, and interstitial infiltrates following one to three doses. Serious outcomes have included respiratory failure and prolonged hospitalization. Patients improved with discontinuation of therapy and in certain cases administration of corticosteroids. If diagnosis is confirmed, discontinue YESINTEK and institute appropriate treatment [see Postmarketing Experience (6.3)].

6 ADVERSE REACTIONS

The following serious adverse reactions are discussed elsewhere in the label:

- Infections [see Warnings and Precautions (5.1)]
- Malignancies [see Warnings and Precautions (5.4)]
- Serious Hypersensitivity Reactions [see Warnings and Precautions (5.5)]
- Posterior Reversible Encephalopathy Syndrome (PRES) [see Warnings and Precautions (5.6)]
- Noninfectious Pneumonia [see Warnings and Precautions (5.8)]

6.1 Clinical Trials Experience

Because clinical trials are conducted under widely varying conditions, adverse reaction rates observed in the clinical trials of a drug cannot be directly compared to rates in the clinical trials of another drug and may not reflect the rates observed in practice.

Adult Subjects with Plaque Psoriasis

The safety data reflect exposure to ustekinumab in 3117 adult subjects with plaque psoriasis, including 2414 exposed for at least 6 months, 1855 exposed for at least one year, 1653 exposed for at least two years, 1569 exposed for at least three years, 1482 exposed for at least four years and 838 exposed for at least five years.

Table 5 summarizes the adverse reactions that occurred at a rate of at least 1% with higher rates in the ustekinumab groups during the placebo-controlled period of Ps STUDY 1 and Ps STUDY 2 [see Clinical Studies (14)].

Table 5: Adverse Reactions, Reported by ≥1% of Subjects with Plaque Psoriasis and at Higher Rates in the ustekinumab groups through Week 12 in Ps STUDY 1 and Ps STUDY 2
 |  | Ustekinumab
 | Placebo | 45 mg | 90 mg
Subjects treated | 665 | 664 | 666
Nasopharyngitis | 51 (8%) | 56 (8%) | 49 (7%)
Upper respiratory tract infection | 30 (5%) | 36 (5%) | 28 (4%)
Headache | 23 (3%) | 33 (5%) | 32 (5%)
Fatigue | 14 (2%) | 18 (3%) | 17 (3%)
Back pain | 8 (1%) | 9 (1%) | 14 (2%)
Dizziness | 8 (1%) | 8 (1%) | 14 (2%)
Pharyngolaryngeal pain | 7 (1%) | 9 (1%) | 12 (2%)
Pruritus | 9 (1%) | 10 (2%) | 9 (1%)
Injection site erythema | 3 (<1%) | 6 (1%) | 13 (2%)
Myalgia | 4 (1%) | 7 (1%) | 8 (1%)
Depression | 3 (<1%) | 8 (1%) | 4 (1%)

Adverse reactions that occurred at rates less than 1% in the controlled period of Ps STUDIES 1 and 2 through week 12 included: cellulitis, herpes zoster, diverticulitis, and certain injection site reactions (pain, swelling, pruritus, induration, hemorrhage, bruising, and irritation).

One case of PRES occurred during clinical trials in adult subjects with plaque psoriasis [see Warnings and Precautions (5.6)].

Infections

In the placebo-controlled period of clinical trials of subjects with plaque psoriasis (average follow-up of 12.6 weeks for subjects receiving placebo and 13.4 weeks for ustekinumab-treated subjects), 27% of ustekinumab-treated subjects reported infections (1.39 per patient-years of follow-up) compared with 24% of subjects receiving placebo (1.21 per patient-years of follow-up). Serious infections occurred in 0.3% of ustekinumab-treated subjects (0.01 per patient-years of follow-up) and in 0.4% of subjects receiving placebo (0.02 per patient-years of follow-up) [see Warnings and Precautions (5.1)].

In the controlled and non-controlled portions of clinical trials in subjects with plaque psoriasis (median follow-up of 3.2 years), representing 8998 patient-years of exposure, 72.3% of ustekinumab-treated subjects reported infections (0.87 per patient-years of follow-up). Serious infections were reported in 2.8% of subjects (0.01 per patient-years of follow-up).

Malignancies

In the controlled and non-controlled portions of clinical trials in subjects with plaque psoriasis (median follow-up of 3.2 years, representing 8998 patient-years of exposure), 1.7% of ustekinumab-treated subjects reported malignancies excluding non-melanoma skin cancers (0.60 per hundred patient-years of follow-up). Non-melanoma skin cancer was reported in 1.5% of ustekinumab-treated subjects (0.52 per hundred patient-years of follow-up) [see Warnings and Precautions (5.4)]. The most frequently observed malignancies other than non-melanoma skin cancer during the clinical trials were: prostate, melanoma, colorectal and breast. Malignancies other than non-melanoma skin cancer in ustekinumab-treated subjects during the controlled and uncontrolled portions of trials were similar in type and number to what would be expected in the general U.S. population according to the SEER database (adjusted for age, gender and race).^1

Pediatric Subjects with Plaque Psoriasis

The safety of ustekinumab was assessed in two trials of pediatric subjects with moderate to severe plaque psoriasis. Ps STUDY 3 evaluated safety for up to 60 weeks in 110 pediatric subjects 12 to 17 years old. Ps STUDY 4 evaluated safety for up to 56 weeks in 44 pediatric subjects 6 to 11 years old. The safety profile in pediatric subjects was similar to the safety profile from trials in adults with plaque psoriasis.

Psoriatic Arthritis

The safety of ustekinumab was assessed in 927 subjects in two randomized, double-blind, placebo-controlled trials in adults with active psoriatic arthritis (PsA). The overall safety profile of ustekinumab in subjects with PsA was consistent with the safety profile seen in clinical trials in adult subjects with plaque psoriasis. A higher incidence of arthralgia, nausea, and dental infections was observed in ustekinumab-treated subjects when compared with placebo-treated subjects (3% vs. 1% for arthralgia and 3% vs. 1% for nausea; 1% vs. 0.6% for dental infections) in the placebo-controlled portions of the PsA clinical trials.

Crohn’s Disease

The safety of ustekinumab was assessed in 1407 subjects with moderately to severely active Crohn’s disease (Crohn’s Disease Activity Index [CDAI] greater than or equal to 220 and less than or equal to 450) in three randomized, double-blind, placebo-controlled, parallel-group, multicenter trials. These 1407 subjects included 40 subjects who received a prior investigational intravenous ustekinumab formulation but were not included in the efficacy analyses. In trials CD-1 and CD- 2 there were 470 subjects who received ustekinumab 6 mg/kg as a weight-based single intravenous induction dose and 466 who received placebo [see Dosage and Administration (2.3)]. Subjects who were responders in either trial CD-1 or CD-2 were randomized to receive a subcutaneous maintenance regimen of either 90 mg ustekinumab every 8 weeks, or placebo for 44 weeks in trial CD-3. Subjects in these 3 trials may have received other concomitant therapies including aminosalicylates, immunomodulatory agents [azathioprine (AZA), 6-mercaptopurine (6-MP), methotrexate (MTX)], oral corticosteroids (prednisone or budesonide), and/or antibiotics for their Crohn’s disease [see Clinical Studies (14.4)].

The overall safety profile of ustekinumab was consistent with the safety profile seen in the clinical trials in adult subjects with plaque psoriasis and psoriatic arthritis. Common adverse reactions in trials CD-1 and CD-2 and in trial CD-3 are listed in Tables 6 and 7, respectively.

Table 6: Common Adverse Reactions Through Week 8 in Trials CD-1 and CD-2 occurring in ≥3% of Ustekinumab - Treated Subjects and Higher Than Subjects Receiving Placebo

 | Placebo | Ustekinumab 6 mg/kg single intravenous induction dose
 | N=466 | N=470
Vomiting | 3% | 4%

Other less common adverse reactions reported in subjects in trials CD-1 and CD-2 included asthenia (1% vs 0.4%), acne (1% vs 0.4%), and pruritus (2% vs 0.4%).

Table 7: Common Adverse Reactions Through Week 44 in Trial CD-3 occurring in ≥3% of Ustekinumab -Treated Subjects and Higher Than Subjects Receiving Placebo

 | Placebo N=133 | Ustekinumab 90 mg subcutaneous maintenance dose every 8 weeks
 |  | N=131
Nasopharyngitis | 8% | 11%
Injection site erythema | 0 | 5%
Vulvovaginal candidiasis/mycotic infection | 1% | 5%
Bronchitis | 3% | 5%
Pruritus | 2% | 4%
Urinary tract infection | 2% | 4%
Sinusitis | 2% | 3%

Infections

In subjects with Crohn's disease, serious or other clinically significant infections included anal abscess, gastroenteritis, and pneumonia. In addition, listeria meningitis and ophthalmic herpes zoster were reported in one subject each [see Warnings and Precautions (5.1)].

Malignancies

With up to one year of treatment in the Crohn's disease clinical trials, 0.2% of ustekinumab-treated subjects (0.36 events per hundred patient-years) and 0.2% of placebo-treated subjects (0.58 events per hundred patient-years) developed non-melanoma skin cancer. Malignancies other than non-melanoma skin cancers occurred in 0.2% of ustekinumab-treated subjects (0.27 events per hundred patient-years) and in none of the placebo-treated subjects.

Hypersensitivity Reactions Including Anaphylaxis

In CD trials, two subjects reported hypersensitivity reactions following ustekinumab administration. One subject experienced signs and symptoms consistent with anaphylaxis (tightness of the throat, shortness of breath, and flushing) after a single subcutaneous administration (0.1% of subjects receiving subcutaneous ustekinumab). In addition, one subject experienced signs and symptoms consistent with or related to a hypersensitivity reaction (chest discomfort, flushing, urticaria, and increased body temperature) after the initial intravenous ustekinumab dose (0.08% of subjects receiving intravenous ustekinumab). These subjects were treated with oral antihistamines or corticosteroids and in both cases symptoms resolved within an hour [see Warnings and Precautions (5.5)].

Ulcerative Colitis

The safety of ustekinumab was evaluated in two randomized, double-blind, placebo-controlled clinical trials (UC-1 [IV induction] and UC-2 [SC maintenance]) in 960 adult subjects with moderately to severely active ulcerative colitis [see Clinical Studies (14.5)]. The overall safety profile of ustekinumab in subjects with ulcerative colitis was consistent with the safety profile seen across all approved indications. Adverse reactions reported in at least 3% of ustekinumab-treated subjects and at a higher rate than placebo were:

- Induction (UC-1): nasopharyngitis (7% vs 4%).
- Maintenance (UC-2): nasopharyngitis (24% vs 20%), headache (10% vs 4%), abdominal pain (7% vs 3%), influenza (6% vs 5%), fever (5% vs. 4%), diarrhea (4% vs 1%), sinusitis (4% vs 1%), fatigue (4% vs 2%), and nausea (3% vs 2%).

Infections

In subjects with ulcerative colitis, serious or other clinically significant infections included gastroenteritis and pneumonia. In addition, listeriosis and ophthalmic herpes zoster were reported in one subject each [see Warnings and Precautions (5.1)].

Malignancies

With up to one year of treatment in the ulcerative colitis clinical trials, 0.4% of ustekinumab-treated subjects (0.48 events per hundred patient-years) and 0.0% of subjects receiving placebo (0.00 events per hundred patient-years) developed non-melanoma skin cancer. Malignancies other than non-melanoma skin cancers occurred in 0.5% of ustekinumab-treated subjects (0.64 events per hundred patient-years) and 0.2% of subjects receiving placebo (0.40 events per hundred patient-years).

6.2 Immunogenicity

The observed incidence of anti-drug antibodies is highly dependent on the sensitivity and specificity of the assay. Differences in assay methods preclude meaningful comparisons of the incidence of anti-drug antibodies in the studies described below with the incidence of anti-drug antibodies in other studies, including those of ustekinumab or of other ustekinumab products. Approximately 6 to 12.4% of subjects treated with ustekinumab in clinical trials in subjects with plaque psoriasis and psoriatic arthritis developed antibodies to ustekinumab, which were generally low-titer. In clinical trials in subjects with plaque psoriasis, antibodies to ustekinumab were associated with reduced or undetectable serum ustekinumab concentrations and reduced efficacy. In trials in subjects with plaque psoriasis, the majority of subjects who were positive for antibodies to ustekinumab had neutralizing antibodies.

In clinical trials in subjects with Crohn’s disease and ulcerative colitis, 2.9% and 4.6% of subjects, respectively, developed antibodies to ustekinumab when treated with ustekinumab for approximately one year. No apparent association between the development of antibodies to ustekinumab and the development of injection site reactions was seen.

6.3 Postmarketing Experience

The following adverse reactions have been reported during post-approval use of ustekinumab products. Because these reactions are reported voluntarily from a population of uncertain size, it is not always possible to reliably estimate their frequency or establish a causal relationship to ustekinumab product exposure.

Immune system disorders: Hypersensitivity reactions (e.g., anaphylaxis, angioedema, dyspnea, rash, urticaria), including a fatal case that presented with chest tightness and dyspnea during infusion of the first dose.

Infections and infestations: Lower respiratory tract infection (including opportunistic fungal infections and tuberculosis).

Neurological disorders: Posterior Reversible Encephalopathy Syndrome (PRES).

Respiratory, thoracic, and mediastinal disorders: Interstitial pneumonia, eosinophilic pneumonia, and cryptogenic organizing pneumonia.

Skin reactions: Pustular psoriasis, erythrodermic psoriasis, hypersensitivity vasculitis.

7 DRUG INTERACTIONS

7.1 Concomitant Therapies

In trials in subjects with plaque psoriasis the safety of ustekinumab products in combination with immunosuppressive agents or phototherapy has not been evaluated. In trials in subjects with psoriatic arthritis, concomitant MTX use did not appear to influence the safety or efficacy of ustekinumab. In trials in subjects with Crohn’s disease (CD-1 and CD-2) and ulcerative colitis (UC-1), immunomodulators (6-MP, AZA, MTX) were used concomitantly in approximately 30% of subjects and corticosteroids were used concomitantly in approximately 40% and 50% of Crohn’s disease and ulcerative colitis subjects, respectively. Use of these concomitant therapies did not appear to influence the overall safety or efficacy of ustekinumab.

7.2 CYP450 Substrates

The formation of CYP450 enzymes can be suppressed by increased levels of certain cytokines (e.g., IL-1, IL-6, TNFα, IFN) during chronic inflammation. Thus, use of ustekinumab products, an antagonist of IL-12 and IL-23, could normalize the formation of CYP450 enzymes. Upon initiation or discontinuation of YESINTEK in patients who are receiving concomitant CYP450 substrates, particularly those with a narrow therapeutic index, consider monitoring for therapeutic effect or drug concentration and adjust the individual dosage of the CYP substrate as needed. See the prescribing information of specific CYP substrates.

A CYP-mediated drug interaction effect was not observed in subjects with Crohn’s disease [see Clinical Pharmacology (12.3)].

7.3 Allergen Immunotherapy

Ustekinumab products have not been evaluated in patients who have undergone allergy immunotherapy. Ustekinumab products may decrease the protective effect of allergen immunotherapy (decrease tolerance) which may increase the risk of an allergic reaction to a dose of allergen immunotherapy. Therefore, caution should be exercised in patients receiving or who have received allergen immunotherapy, particularly for anaphylaxis.

8 USE IN SPECIFIC POPULATIONS

8.1 Pregnancy

Risk Summary

Available data from the Organization of Teratology Information Specialists (OTIS)/MotherToBaby Pregnancy Registry, published literature and pharmacovigilance in pregnant women have not identified a ustekinumab-associated risk of major birth defects, miscarriage or other adverse maternal or fetal outcomes (see Data). There are risks to the mother and the fetus associated with inflammatory bowel disease (IBD) in pregnancy. In animal reproductive and developmental toxicity studies, no adverse developmental effects were observed in offspring after administration of ustekinumab to pregnant monkeys at exposures greater than 100 times the maximum recommended human dose (MRHD).

All pregnancies have a background risk of birth defect, loss, or other adverse outcomes. In the U.S. general population, the estimated background risk of major birth defects and miscarriage of clinically recognized pregnancies is 2% to 4% and 15% to 20%, respectively.

Clinical Considerations

Disease-associated Maternal and Embryo/Fetal Risk

Published data suggest that the risk of adverse pregnancy outcomes in women with IBD is associated with increased disease activity. Adverse pregnancy outcomes include preterm delivery (before 37 weeks of gestation), low birth weight (less than 2500 g) infants, and small for gestational age at birth.

Fetal/Neonatal Adverse Reactions

Transport of endogenous IgG antibodies across the placenta increases as pregnancy progresses, and peaks during the third trimester. Therefore, ustekinumab products may be present in infants exposed in utero. The potential clinical impact of ustekinumab product exposure in infants exposed in utero should be considered.

Data

Human Data

An observational pregnancy registry conducted by (OTIS)/MotherToBaby in the U.S. and Canada (enrollment between 2013 and 2019) assessed the risk of major birth defects, pattern of major and minor anomalies in live-born infants, miscarriage, and adverse infant outcomes in women with ustekinumab exposure. In the registry study, there were 101 participants and 107 pregnancies with exposure to ustekinumab (88 prospective; 19 retrospective). Most participants had a primary indication of CD (65.4%) or psoriasis (30.8%). The pregnancy registry did not identify a ustekinumab -associated risk of major birth defects, pattern of major or minor anomalies, increased risk of miscarriage or adverse infant outcomes. Methodological limitations of the registry include small sample size, lack of an internal comparison group, a mix of prospective and retrospective reports, and unmeasured confounders. The conclusions from the pregnancy registry were consistent with the published literature and pharmacovigilance.

Animal Data

Ustekinumab was tested in two embryo-fetal development toxicity studies in cynomolgus monkeys. No teratogenic or other adverse developmental effects were observed in fetuses from pregnant monkeys that were administered ustekinumab subcutaneously twice weekly or intravenously weekly during the period of organogenesis. Serum concentrations of ustekinumab in pregnant monkeys were greater than 100 times the serum concentration in patients treated subcutaneously with 90 mg of ustekinumab weekly for 4 weeks.

In a combined embryo-fetal development and pre- and post-natal development toxicity study, pregnant cynomolgus monkeys were administered subcutaneous doses of ustekinumab twice weekly at exposures greater than 100 times the MRHD from the beginning of organogenesis to Day 33 after delivery. Neonatal deaths occurred in the offspring of one monkey administered ustekinumab at 22.5 mg/kg and one monkey dosed at 45 mg/kg. No ustekinumab-related-effects on functional, morphological, or immunological development were observed in the neonates from birth through six months of age.

8.2 Lactation

Risk Summary

Limited data from published literature suggests that ustekinumab is present in human breast milk. There are no available data on the effects of ustekinumab products on milk production. The effects of local gastrointestinal exposure and limited systemic exposure in the breastfed infant to ustekinumab products are unknown. No adverse effects on the breastfed infant causally related to ustekinumab products have been identified in the published literature or postmarketing experience.

The developmental and health benefits of breastfeeding should be considered along with the mother’s clinical need for YESINTEK and any potential adverse effects on the breastfed child from YESINTEK or from the underlying maternal condition.

8.4 Pediatric Use

Plaque Psoriasis

The safety and effectiveness of YESINTEK have been established for the treatment of moderate to severe plaque psoriasis in pediatric patients 6 years of age and older who are candidates for phototherapy or systemic therapy.

Use of YESINTEK in pediatric patients 12 to less than 17 years of age is supported by evidence from a multicenter, randomized, 60 week trial (Ps STUDY 3) of ustekinumab that included a 12-week, double-blind, placebo-controlled, parallel group portion, in 110 pediatric subjects 12 years of age and older [see Adverse Reactions (6.1), Clinical Studies (14.2)].

Use of YESINTEK in pediatric patients 6 to 11 years of age is supported by evidence from an open-label, single-arm, efficacy, safety, and pharmacokinetics trial (Ps STUDY 4) of ustekinumab in 44 subjects [see Adverse Reactions (6.1), Pharmacokinetics (12.3)].

The safety and effectiveness of YESINTEK have not been established in pediatric patients less than 6 years of age with plaque psoriasis.

Psoriatic Arthritis

The safety and effectiveness of YESINTEK have been established for treatment of psoriatic arthritis in pediatric patients 6 years of age and older.

Use of YESINTEK in these age groups is supported by evidence from adequate and well controlled trials of ustekinumab in adult subjects with psoriasis and PsA, pharmacokinetic data from adult subjects with psoriasis, adult subjects with PsA and pediatric subjects with psoriasis, and safety data of ustekinumab from two clinical trials in 44 pediatric subjects 6 to 11 years old with psoriasis and 110 pediatric subjects 12 years of age and older with psoriasis. The observed pre-dose (trough) concentrations are generally comparable between adult subjects with psoriasis, adult subjects with PsA and pediatric subjects with psoriasis, and the PK exposure is expected to be comparable between adult and pediatric subjects with PsA [see Adverse Reactions (6.1), Clinical Pharmacology (12.3), and Clinical Studies (14.1, 14.2, 14.3)].

The safety and effectiveness of YESINTEK have not been established in pediatric patients less than 6 years old with psoriatic arthritis.

Crohn’s Disease and Ulcerative Colitis

The safety and effectiveness of YESINTEK have not been established in pediatric patients with Crohn’s disease or ulcerative colitis.

8.5 Geriatric Use

Of the 6709 subjects exposed to ustekinumab, a total of 340 were 65 years of age or older (183 subjects with plaque psoriasis, 65 subjects with psoriatic arthritis, 58 subjects with Crohn’s disease, and 34 subjects with ulcerative colitis), and 40 subjects were 75 years of age or older. Clinical trials of ustekinumab did not include sufficient numbers of subjects 65 years of age and older to determine whether they respond differently from younger adult subjects.

10 OVERDOSAGE

Single doses up to 6 mg/kg intravenously have been administered in clinical trials without dose-limiting toxicity. In case of overdosage, monitor the patient for any signs or symptoms of adverse reactions or effects and institute appropriate symptomatic treatment immediately. Consider contacting the Poison Help line 1-800-222-1222 or a medical toxicologist for additional overdose management recommendations.

11 DESCRIPTION

Ustekinumab-kfce, a human IgG1κ monoclonal antibody, is a human interleukin-12 and -23 antagonist. Using DNA recombinant technology, ustekinumab-kfce is produced in a murine cell line (Sp2/0). The manufacturing process contains steps for the clearance of viruses. Ustekinumab is comprised of 1326 amino acids and has an estimated molecular mass that ranges from 148,079 to 149,690 Daltons.

YESINTEK (ustekinumab-kfce) injection is a sterile, preservative-free, clear and colorless to pale yellow solution with pH of 5.7- 6.3.

YESINTEK for Subcutaneous Use

Available as 45 mg of ustekinumab-kfce in 0.5 mL and 90 mg of ustekinumab-kfce in 1 mL, supplied as a sterile solution in a single-dose prefilled syringe with a 29 gauge fixed ½ inch needle and as 45 mg of ustekinumab-kfce in 0.5 mL in a single-dose Type I glass vial with a coated stopper. The syringe is fitted with a passive needle guard and a needle cover.

Each 0.5 mL prefilled syringe or vial delivers 45 mg ustekinumab-kfce, histidine, L-histidine monohydrochloride monohydrate (0.5 mg), Polysorbate 80 (0.02 mg), and sucrose (38 mg). Hydrochloric acid and sodium hydroxide are used to adjust pH to 5.7- 6.3 during manufacturing.

Each 1 mL prefilled syringe delivers 90 mg ustekinumab-kfce, histidine, L-histidine monohydrochloride monohydrate (1 mg), Polysorbate 80 (0.04 mg), and sucrose (76 mg). Hydrochloric acid and sodium hydroxide are used to adjust pH to 5.7- 6.3 during manufacturing.

YESINTEK for Intravenous Infusion

Available as 130 mg of ustekinumab-kfce in 26 mL, supplied as a single-dose Type I glass vial with a coated stopper.

Each 26 mL vial delivers 130 mg ustekinumab-kfce, edetate disodium (0.47 mg), histidine (20 mg), L-histidine hydrochloride monohydrate (27 mg), methionine (10.4 mg), Polysorbate 80 (10.4 mg), and sucrose (2210 mg). Hydrochloric acid and sodium hydroxide added to adjust the pH to 5.7- 6.3 during manufacturing.

12 CLINICAL PHARMACOLOGY

12.1 Mechanism of Action

Ustekinumab products are human IgG1қ monoclonal antibodies that binds with specificity to the p40 protein subunit used by both the IL-12 and IL-23 cytokines. IL-12 and IL-23 are naturally occurring cytokines that are involved in inflammatory and immune responses, such as natural killer cell activation and CD4+ T-cell differentiation and activation. In in vitro models, ustekinumab products were shown to disrupt IL-12 and IL-23 mediated signaling and cytokine cascades by disrupting the interaction of these cytokines with a shared cell-surface receptor chain, IL-12Rβ1. The cytokines IL-12 and IL-23 have been implicated as important contributors to the chronic inflammation that is a hallmark of Crohn’s disease and ulcerative colitis. In animal models of colitis, genetic absence or antibody blockade of the p40 subunit of IL-12 and IL-23, the target of ustekinumab products, was shown to be protective.

12.2 Pharmacodynamics

Plaque Psoriasis

In a small exploratory trial, a decrease was observed in the expression of mRNA of its molecular targets IL-12 and IL-23 in lesional skin biopsies measured at baseline and up to two weeks post-treatment in subjects with plaque psoriasis.

Ulcerative Colitis

In both trial UC-1 (induction) and trial UC-2 (maintenance), a positive relationship was observed between exposure and rates of clinical remission, clinical response, and endoscopic improvement. The response rate approached a plateau at the ustekinumab exposures associated with the recommended dosing regimen for maintenance treatment [see Clinical Studies (14.5)].

12.3 Pharmacokinetics

Absorption

In adult subjects with plaque psoriasis, the median time to reach the maximum serum concentration (Tmax) was 13.5 days and 7 days, respectively, after a single subcutaneous administration of 45 mg (N=22) and 90 mg (N=24) of ustekinumab. In healthy subjects (N=30), the median Tmax value (8.5 days) following a single subcutaneous administration of 90 mg of ustekinumab was comparable to that observed in subjects with plaque psoriasis.

Following multiple subcutaneous doses of ustekinumab in adult subjects with plaque psoriasis, steady-state serum concentrations of ustekinumab were achieved by Week 28. The mean (±SD) steady-state trough serum ustekinumab concentrations were 0.69 ± 0.69 mcg/mL for subjects less than or equal to 100 kg receiving a 45 mg dose and 0.74 ± 0.78 mcg/mL for subjects greater than 100 kg receiving a 90 mg dose. There was no apparent accumulation in serum ustekinumab concentration over time when given subcutaneously every 12 weeks.

Following the recommended intravenous induction dose, mean ±SD peak serum ustekinumab concentration was 125.2 ± 33.6 mcg/mL in subjects with Crohn's disease, and 129.1 ± 27.6 mcg/mL in subjects with ulcerative colitis. Starting at Week 8, the recommended subcutaneous maintenance dosing of 90 mg ustekinumab was administered every 8 weeks. Steady state ustekinumab concentration was achieved by the start of the second maintenance dose. There was no apparent accumulation in ustekinumab concentration over time when given subcutaneously every 8 weeks. Mean ±SD steady-state trough concentration was 2.5 ± 2.1 mcg/mL in subjects with Crohn's disease, and 3.3 ± 2.3 mcg/mL in subjects with ulcerative colitis for 90 mg ustekinumab administered every 8 weeks.

Distribution

Population pharmacokinetic analyses showed that the volume of distribution of ustekinumab in the central compartment was 2.7 L (95% CI: 2.69, 2.78) in subjects with Crohn's disease and 3.0 L (95% CI: 2.96, 3.07) in subjects with ulcerative colitis. The total volume of distribution at steady-state was 4.6 L in subjects with Crohn's disease and 4.4 L in subjects with ulcerative colitis.

Elimination

The mean (±SD) half-life ranged from 14.9 ± 4.6 to 45.6 ± 80.2 days across all trials in subjects with plaque psoriasis following subcutaneous administration. Population pharmacokinetic analyses showed that the clearance of ustekinumab was 0.19 L/day (95% CI: 0.185, 0.197) in subjects with Crohn’s disease and 0.19 L/day (95% CI: 0.179, 0.192) in subjects with ulcerative colitis with an estimated median terminal half-life of approximately 19 days for both IBD (Crohn’s disease and ulcerative colitis) populations.

These results indicate the pharmacokinetics of ustekinumab were similar between subjects with Crohn’s disease and ulcerative colitis.

Metabolism

The metabolic pathway of ustekinumab products has not been characterized. As a human IgG1κ monoclonal antibody, ustekinumab product are expected to be degraded into small peptides and amino acids via catabolic pathways in the same manner as endogenous IgG.

Specific Populations

Weight

When given the same dose, subjects with plaque psoriasis or psoriatic arthritis weighing more than 100 kg had lower median serum ustekinumab concentrations compared with those subjects weighing 100 kg or less. The median trough serum concentrations of ustekinumab in subjects of higher weight (greater than 100 kg) in the 90 mg group were comparable to those in subjects of lower weight (100 kg or less) in the 45 mg group.

Age: Geriatric Population

A population pharmacokinetic analysis (N=106/1937 subjects with plaque psoriasis greater than or equal to 65 years old) was performed to evaluate the effect of age on the pharmacokinetics of ustekinumab. There were no apparent changes in pharmacokinetic parameters (clearance and volume of distribution) in subjects older than 65 years old.

Age: Pediatric Population

Following multiple recommended doses of ustekinumab in pediatric subjects 6 years of age and older with plaque psoriasis, steady-state serum concentrations of ustekinumab were achieved by Week 28. At Week 28, the mean ±SD steady-state trough serum ustekinumab concentrations were 0.36 ± 0.26 mcg/mL and 0.54 ± 0.43 mcg/mL, respectively, in pediatric subjects 6 to 11 years of age and pediatric subjects 12 years of age and older.

Overall, the observed steady-state ustekinumab trough concentrations in pediatric subjects with plaque psoriasis were within the range of those observed for adult subjects with plaque psoriasis and adult subjects with PsA after administration of ustekinumab.

Drug Interaction Studies

The effects of IL-12 or IL-23 on the regulation of CYP450 enzymes were evaluated in an in vitro study using human hepatocytes, which showed that IL-12 and/or IL-23 at levels of 10 ng/mL did not alter human CYP450 enzyme activities (CYP1A2, 2B6, 2C9, 2C19, 2D6, or 3A4).

No clinically significant changes in exposure of caffeine (CYP1A2 substrate), warfarin (CYP2C9 substrate), omeprazole (CYP2C19 substrate), dextromethorphan (CYP2D6 substrate), or midazolam (CYP3A substrate) were observed when used concomitantly with ustekinumab at the approved recommended dosage in subjects with Crohn’s disease [see Drug Interactions (7.2)].

Population pharmacokinetic analyses indicated that the clearance of ustekinumab was not impacted by concomitant MTX, NSAIDs, and oral corticosteroids, or prior exposure to a TNF blocker in subjects with psoriatic arthritis.

In subjects with Crohn's disease and ulcerative colitis, population pharmacokinetic analyses did not indicate changes in ustekinumab clearance with concomitant use of corticosteroids or immunomodulators (AZA, 6-MP, or MTX); and serum ustekinumab concentrations were not impacted by concomitant use of these medications.

13 NONCLINICAL TOXICOLOGY

13.1 Carcinogenesis, Mutagenesis, Impairment of Fertility

Animal studies have not been conducted to evaluate the carcinogenic or mutagenic potential of ustekinumab products. Published literature showed that administration of murine IL-12 caused an anti-tumor effect in mice that contained transplanted tumors and IL-12/IL-23p40 knockout mice or mice treated with anti-IL-12/IL-23p40 antibody had decreased host defense to tumors. Mice genetically manipulated to be deficient in both IL-12 and IL-23 or IL-12 alone developed UV-induced skin cancers earlier and more frequently compared to wild-type mice. The relevance of these experimental findings in mouse models for malignancy risk in humans is unknown.

No effects on fertility were observed in male cynomolgus monkeys that were administered ustekinumab at subcutaneous doses up to 45 mg/kg twice weekly (45 times the MRHD on a mg/kg basis) prior to and during the mating period. However, fertility and pregnancy outcomes were not evaluated in mated females.

No effects on fertility were observed in female mice that were administered an analogous IL-12/IL-23p40 antibody by subcutaneous administration at doses up to 50 mg/kg, twice weekly, prior to and during early pregnancy.

13.2 Animal Toxicology and/or Pharmacology

In a 26-week toxicology study, one out of 10 monkeys subcutaneously administered 45 mg/kg ustekinumab twice weekly for 26 weeks had a bacterial infection.

14 CLINICAL STUDIES

14.1 Adult Subjects with Plaque Psoriasis

Two multicenter, randomized, double-blind, placebo-controlled trials (Ps STUDY 1 and Ps STUDY 2) enrolled a total of 1996 subjects 18 years of age and older with plaque psoriasis who had a minimum body surface area involvement of 10%, and Psoriasis Area and Severity Index (PASI) score ≥12, and who were candidates for phototherapy or systemic therapy. Subjects with guttate, erythrodermic, or pustular psoriasis were excluded from the trials.

Ps STUDY 1 enrolled 766 subjects and Ps STUDY 2 enrolled 1230 subjects. The trials had the same design through Week 28. In both trials, subjects were randomized in equal proportion to placebo, 45 mg or 90 mg of ustekinumab. Subjects randomized to ustekinumab received 45 mg or 90 mg doses, regardless of weight, at Weeks 0, 4, and 16. Subjects randomized to receive placebo at Weeks 0 and 4 crossed over to receive ustekinumab (either 45 mg or 90 mg) at Weeks 12 and 16.

In both trials, subjects in all treatment groups had a median baseline PASI score ranging from approximately 17 to 18. Baseline PGA score was marked or severe in 44% of subjects in Ps STUDY 1 and 40% of subjects in Ps STUDY 2. Approximately two-thirds of all subjects had received prior phototherapy, 69% had received either prior conventional systemic or biologic therapy for the treatment of psoriasis, with 56% receiving prior conventional systemic therapy and 43% receiving prior biologic therapy. A total of 28% of subjects had a history of psoriatic arthritis.

In both trials, the endpoints were the proportion of subjects who achieved at least a 75% reduction in PASI score (PASI 75) from baseline to Week 12 and treatment success (cleared or minimal) on the Physician’s Global Assessment (PGA). The PGA is a 6-category scale ranging from 0 (cleared) to 5 (severe) that indicates the physician’s overall assessment of psoriasis focusing on plaque thickness/induration, erythema, and scaling.

Clinical Response

The results of Ps STUDY 1 and Ps STUDY 2 are presented in Table 8 below.

Table 8: Clinical Outcomes at Week 12 in Adult Subjects with Plaque Psoriasis in Ps STUDY 1 and Ps STUDY 2

 | Ps STUDY 1 |  |  | Ps STUDY 2
 | Ustekinumab |  |  | Ustekinumab
 | Placebo | 45 mg | 90 mg | Placebo | 45 mg | 90 mg
Subjects randomized | 255 | 255 | 256 | 410 | 409 | 411
PASI 75 response | 8 (3%) | 171 (67%) | 170 (66%) | 15 (4%) | 273 (67%) | 311 (76%)
PGA of Cleared or Minimal | 10 (4%) | 151 (59%) | 156 (61%) | 18 (4%) | 277 (68%) | 300 (73%)

Examination of age, gender, and race subgroups did not identify differences in response to ustekinumab among these subgroups.

In subjects who weighed 100 kg or less, response rates were comparable with both the 45 mg and 90 mg doses; however, in subjects who weighed greater than 100 kg, higher response rates were seen with 90 mg dosing compared with 45 mg dosing (Table 9 below).

Table 9: Clinical Outcomes by Weight at Week 12 in Adult Subjects with Plaque Psoriasis in Ps STUDY 1 and Ps STUDY 2
 | Ps STUDY 1 |  |  | Ps STUDY 2
 | Ustekinumab |  |  | Ustekinumab
 | Placebo | 45 mg | 90 mg | Placebo | 45 mg | 90 mg
Subjects randomized | 255 | 255 | 256 | 410 | 409 | 411
PASI 75 response [Subjects were dosed with trial medication at Weeks 0 and 4.]
≤100 kg | 4% | 74% | 65% | 4% | 73% | 78%
 | 6/166 | 124/168 | 107/164 | 12/290 | 218/297 | 225/289
>100 kg | 2% | 54% | 68% | 3% | 49% | 71%
 | 2/89 | 47/87 | 63/92 | 3/120 | 55/112 | 86/121
PGA of Cleared or Minimal
≤100 kg | 4% | 64% | 63% | 5% | 74% | 75%
 | 7/166 | 108/168 | 103/164 | 14/290 | 220/297 | 216/289
>100 kg | 3% | 49% | 58% | 3% | 51% | 69%
 | 3/89 | 43/87 | 53/92 | 4/120 | 57/112 | 84/121

Subjects in Ps STUDY 1 who were PASI 75 responders at both Weeks 28 and 40 were re-randomized at Week 40 to either continued dosing of ustekinumab (ustekinumab at Week 40) or to withdrawal of therapy (placebo at Week 40). At Week 52, 89% (144/162) of subjects re-randomized to ustekinumab treatment were PASI 75 responders compared with 63% (100/159) of subjects re-randomized to placebo (treatment withdrawal after Week 28 dose). The median time to loss of PASI 75 response among the subjects randomized to treatment withdrawal was 16 weeks.

14.2 Pediatric Subjects with Plaque Psoriasis

A multicenter, randomized, double blind, placebo-controlled trial (Ps STUDY 3) enrolled 110 pediatric subjects 12 years of age and older with a minimum BSA involvement of 10%, a PASI score greater than or equal to 12, and a PGA score greater than or equal to 3, who were candidates for phototherapy or systemic therapy and whose disease was inadequately controlled by topical therapy

Subjects were randomized to receive placebo (n = 37), the recommended dose of ustekinumab (n = 36), or one-half the recommended dose of ustekinumab (n = 37) by subcutaneous injection at Weeks 0 and 4 followed by dosing every 12 weeks (q12w). The recommended dose of ustekinumab was 0.75 mg/kg for subjects weighing less than 60 kg, 45 mg for subjects weighing 60 kg to 100 kg, and 90 mg for subjects weighing greater than 100 kg. At Week 12, subjects who received placebo were crossed over to receive ustekinumab at the recommended dose or one-half the recommended dose.

Of the pediatric subjects, approximately 63% had prior exposure to phototherapy or conventional systemic therapy and approximately 11% had prior exposure to biologics.

The endpoints were the proportion of subjects who achieved a PGA score of cleared (0) or minimal (1), PASI 75, and PASI 90 at Week 12. Subjects were followed for up to 60 weeks following first administration of trial agent.

Clinical Response

The efficacy results at Week 12 for Ps STUDY 3 are presented in Table 10.

Table 10: Efficacy Results at Week 12 in Pediatric Subjects 12 Years of Age and Older with Plaque Psoriasis in Ps STUDY 3
 | Ps STUDY 3
 | Placebo n (%) | Ustekinumab [Using the weight-based dosage regimen specified in Table 1 and Table 2.] n%
N | 37 | 36
PGA
PGA of cleared (0) or minimal (1) | 2 (5.4%) | 25 (69.4%)
PASI
PASI 75 responders | 4 (10.8%) | 29 (80.6%)
PASI 90 responders | 2 (5.4%) | 22 (61.1%)

14.3 Psoriatic Arthritis

The safety and efficacy of ustekinumab was assessed in 927 subjects (PsA STUDY 1, n=615; PsA STUDY 2, n=312), in two randomized, double-blind, placebo-controlled trials in adult subjects 18 years of age and older with active PsA (≥5 swollen joints and ≥5 tender joints) despite non-steroidal anti-inflammatory (NSAID) or disease modifying antirheumatic (DMARD) therapy. Subjects in these trials had a diagnosis of PsA for at least 6 months. Subjects with each subtype of PsA were enrolled, including polyarticular arthritis with the absence of rheumatoid nodules (39%), spondylitis with peripheral arthritis (28%), asymmetric peripheral arthritis (21%), distal interphalangeal involvement (12%) and arthritis mutilans (0.5%). Over 70% and 40% of the patients, respectively, had enthesitis and dactylitis at baseline.

Subjects were randomized to receive treatment with ustekinumab 45 mg, 90 mg, or placebo subcutaneously at Weeks 0 and 4 followed by every 12 weeks (q12w) dosing. Approximately 50% of subjects continued on stable doses of MTX (≤25 mg/week). The primary endpoint was the percentage of subjects achieving ACR 20 response at Week 24.

In PsA STUDY 1 and PsA STUDY 2, 80% and 86% of the subjects, respectively, had been previously treated with DMARDs. In PsA STUDY 1, previous treatment with anti-tumor necrosis factor (TNF)-α agent was not allowed. In PsA STUDY 2, 58% (n=180) of the subjects had been previously treated with TNF blocker, of whom over 70% had discontinued their TNF blocker treatment for lack of efficacy or intolerance at any time.

Clinical Response

In both trials, a greater proportion of subjects achieved ACR 20, ACR 50 and PASI 75 response in the ustekinumab 45 mg and 90 mg groups compared to placebo at Week 24 (see Table 11). ACR 70 responses were also higher in the ustekinumab 45 mg and 90 mg groups, although the difference was only numerical (p=NS) in STUDY 2. Responses were consistent in subjects treated with ustekinumab alone or in combination with methotrexate. Responses were similar in subjects regardless of prior TNFα exposure.

Table 11: ACR 20, ACR 50, ACR 70 and PASI 75 Responses In PsA STUDY 1 And PsA STUDY 2 At Week 24
 | PsA STUDY 1 |  |  | PsA STUDY 2
 | Ustekinumab |  |  | Ustekinumab
 | Placebo | 45 mg | 90 mg | Placebo | 45 mg | 90 mg
Number of subjects randomized | 206 | 205 | 204 | 104 | 103 | 105
ACR 20 response, N (%) | 47 (23%) | 87 (42%) | 101 (50%) | 21 (20%) | 45 (44%) | 46 (44%)
ACR 50 response, N (%) | 18 (9%) | 51 (25%) | 57 (28%) | 7 (7%) | 18 (17%) | 24 (23%)
ACR 70 response, N (%) | 5 (2%) | 25 (12%) | 29 (14%) | 3 (3%) | 7 (7%) | 9 (9%)
Number of subjects with ≥ 3% BSA [Number of subjects with ≥ 3% BSA psoriasis skin involvement at baseline] | 146 | 145 | 149 | 80 | 80 | 81
PASI 75 response, N (%) | 16 (11%) | 83 (57%) | 93 (62%) | 4 (5%) | 41 (51%) | 45 (56%)

The percent of subjects achieving ACR 20 responses by visit is shown in Figure 1.

Figure 1: Percent of subjects achieving ACR 20 response through Week 24

PsA STUDY 1

The results of the components of the ACR response criteria are shown in Table 12.

Table 12: Mean Change From Baseline In ACR Components At Week 24

PsA STUDY 1
Ustekinumab
 | Placebo; (N = 206) | 45 mg; (N = 205) | 90 mg; (N = 204)
Number of swollen jointsa
Baseline | 15 | 12 | 13
Mean Change at Week 24 | -3 | -5 | -6
Number of tender jointsb
Baseline | 25 | 22 | 23
Mean Change at Week 24 | -4 | -8 | -9
Subject’s assessment of painc
Baseline | 6.1 | 6.2 | 6.6
Mean Change at Week 24 | -0.5 | -2.0 | -2.6
Subject global assessmentc
Baseline | 6.1 | 6.3 | 6.4
Mean Change at Week 24 | -0.5 | -2.0 | -2.5
Physician global assessmentc
Baseline | 5.8 | 5.7 | 6.1
Mean Change at Week 24 | -1.4 | -2.6 | -3.1
Disability index (HAQ)d
Baseline | 1.2 | 1.2 | 1.2
Mean Change at Week 24 | -0.1 | -0.3 | -0.4
CRP (mg/dL) e
Baseline | 1.6 | 1.7 | 1.8
Mean Change at Week 24 | 0.01 | -0.5 | -0.8

a Number of swollen joints counted (0-66)

b Number of tender joints counted (0-68)

c Visual analogue scale; 0= best, 10=worst.

d Disability Index of the Health Assessment Questionnaire; 0 = best, 3 = worst, measures the patient’s ability to perform the following: dress/groom, arise, eat, walk, reach, grip, maintain hygiene, and maintain daily activity.

e CRP: (Normal Range 0.0-1.0 mg/dL)

An improvement in enthesitis and dactylitis scores was observed in each ustekinumab group compared with placebo at Week 24.

Physical Function

Ustekinumab-treated subjects showed improvement in physical function compared to subjects receiving placebo as assessed by HAQ-DI at Week 24. In both trials, the proportion of HAQ-DI responders (≥0.3 improvement in HAQ-DI score) was greater in the ustekinumab 45 mg and 90 mg groups compared to placebo at Week 24.

14.4 Crohn's Disease

Ustekinumab was evaluated in three randomized, double-blind, placebo-controlled clinical trials in adult subjects with moderately to severely active Crohn's disease (Crohn's Disease Activity Index [CDAI] score of 220 to 450). There were two 8-week intravenous induction trials (CD-1 and CD-2) followed by a 44-week subcutaneous randomized withdrawal maintenance trial (CD-3) representing 52 weeks of therapy. Subjects in CD-1 had failed or were intolerant to treatment with one or more TNF blockers, while subjects in CD-2 had failed or were intolerant to treatment with immunomodulators or corticosteroids, but never failed treatment with a TNF blocker.

Trials CD-1 and CD-2

In trials CD-1 and CD-2, 1409 subjects were randomized, of whom 1368 (CD-1, n=741; CD-2, n=627) were included in the final efficacy analysis. Induction of clinical response (defined as a reduction in CDAI score of greater than or equal to 100 points or CDAI score of less than 150) at Week 6 and clinical remission (defined as a CDAI score of less than 150) at Week 8 were evaluated. In both trials, subjects were randomized to receive a single intravenous administration of ustekinumab at either approximately 6 mg/kg, placebo (see Table 4), or 130 mg (a lower dose than recommended).

In trial CD-1, subjects had failed or were intolerant to prior treatment with a TNF blocker: 29% subjects had an inadequate initial response (primary non-responders), 69% responded but subsequently lost response (secondary non-responders) and 36% were intolerant to a TNF blocker. Of these subjects, 48% failed or were intolerant to one TNF blocker and 52% had failed 2 or 3 prior TNF blockers. At baseline and throughout the trial, approximately 46% of the subjects were receiving corticosteroids and 31% of the subjects were receiving immunomodulators (AZA, 6-MP, MTX). The median baseline CDAI score was 319 in the ustekinumab approximately 6 mg/kg group and 313 in the placebo group.

In trial CD-2, subjects had failed or were intolerant to prior treatment with corticosteroids (81% of subjects), at least one immunomodulator (6-MP, AZA, MTX; 68% of subjects), or both (49% of subjects). Additionally, 69% never received a TNF blocker and 31% previously received but had not failed a TNF blocker. At baseline, and throughout the trial, approximately 39% of the subjects were receiving corticosteroids and 35% of the subjects were receiving immunomodulators (AZA, 6-MP, MTX). The median baseline CDAI score was 286 in the ustekinumab and 290 in the placebo group.

In these induction trials, a greater proportion of subjects treated with ustekinumab (at the recommended dose of approximately 6 mg/kg dose) achieved clinical response at Week 6 and clinical remission at Week 8 compared to placebo (see Table 13 for clinical response and remission rates). Clinical response and remission were significant as early as Week 3 in ustekinumab-treated subjects and continued to improve through Week 8.

Table 13: Induction of Clinical Response and Remission in CD-1* and CD-2**

 | CD-1; n = 741 |  |  | CD-2; n = 627
 | Placebo N = 247 | Ustekinumab †; N = 249 | Treatment difference; and 95% CI | Placebo N = 209 | Ustekinumab †; N = 209 | Treatment difference; and 95% CI
Clinical Response; (100 point), Week 6 | 53 (21%) | 84 (34%)a | 12%; (4%, 20%) | 60 (29%) | 116 (56%)b | 27%; (18%, 36%)
Clinical Remission,; Week 8 | 18 (7%) | 52 (21%)b | 14%; (8%, 20%) | 41 (20%) | 84 (40%)b | 21%; (12%, 29%)
Clinical Response; (100 point), Week 8 | 50 (20%) | 94 (38%)b | 18%; (10%, 25%) | 67 (32%) | 121 (58%)b | 26%; (17%, 35%)
70 Point Response,; Week 6 | 75 (30%) | 109 (44%)a | 13%; (5%, 22%) | 81 (39%) | 135 (65%)b | 26%; (17%, 35%)
70 Point Response,; Week 3 | 67 (27%) | 101 (41%)a | 13%; (5%, 22%) | 66 (32%) | 106 (51%)b | 19%; (10%, 28%)

Clinical remission is defined as CDAI score < 150; Clinical response is defined as reduction in CDAI score by at least 100 points or being in clinical remission: 70 point response is defined as reduction in CDAI score by at least 70 points

* Patient population consisted of subjects who failed or were intolerant to TNF blocker therapy

** Patient population consisted of subjects who failed or were intolerant to corticosteroids or immunomodulators (e.g., 6-MP, AZA, MTX) and previously received but not failed a TNF blocker or were never treated with a TNF blocker.

† Infusion dose of ustekinumab using the weight-based dosage regimen specified in Table 4.

a 0.001≤ p < 0.01

b p < 0.001

Trial CD-3

The maintenance trial (CD-3), evaluated 388 subjects who achieved clinical response (≥100 point reduction in CDAI score) at Week 8 with either induction dose of ustekinumab in trials CD-1 or CD-2. Subjects were randomized to receive a subcutaneous maintenance regimen of either 90 mg ustekinumab every 8 weeks or placebo for 44 weeks (see Table 14).

Table 14: Clinical Response and Remission In CD-3 (Week 44; 52 Weeks From Initiation Of Induction Dose)

 | Placebo*; N = 131† | 90 mg Ustekinumab every 8 weeks; N = 128† | Treatment difference and; 95% CI
Clinical Remission | 47 (36%) | 68 (53%)a | 17% (5%, 29%)
Clinical Response | 58 (44%) | 76 (59%)b | 15% (3%, 27%)
Clinical Remission in patients in remission at the start of maintenance therapy** | 36/79 (46%) | 52/78 (67%)a | 21% (6%, 36%)

Clinical remission is defined as CDAI score < 150; Clinical response is defined as reduction in CDAI of at least 100 points or being in clinical remission

* The placebo group consisted of subjects who were in response to ustekinumab and were randomized to receive placebo at the start of maintenance therapy.

** Subjects in remission at the end of maintenance therapy who were in remission at the start of maintenance

therapy. This does not account for any other time point during maintenance therapy.

† Subjects who achieved clinical response to ustekinumab at the end of the induction trial.

a p < 0.01

b 0.01≤ p < 0.05

At Week 44, 47% of subjects who received ustekinumab were corticosteroid-free and in clinical remission, compared to 30% of subjects in the placebo group.

At Week 0 of trial CD-3, 34/56 (61%) ustekinumab-treated subjects who previously failed or were intolerant to TNF blocker therapies were in clinical remission and 23/56 (41%) of these subjects were in clinical remission at Week 44. In the placebo arm, 27/61 (44%) subjects were in clinical remission at Week 0 while 16/61 (26%) of these subjects were in remission at Week 44.

At Week 0 of trial CD-3, 46/72 (64%) ustekinumab-treated subjects who had previously failed immunomodulator therapy or corticosteroids (but not TNF blockers) were in clinical remission and 45/72 (63%) of these subjects were in clinical remission at Week 44. In the placebo arm, 50/70 (71%) of these subjects were in clinical remission at Week 0 while 31/70 (44%) were in remission at Week 44. In the subset of these subjects who were also naïve to TNF blockers, 34/52 (65%) of ustekinumab-treated subjects were in clinical remission at Week 44 as compared to 25/51 (49%) in the placebo arm.

Subjects who were not in clinical response 8 weeks after ustekinumab induction were not included in the primary efficacy analyses for trial CD-3; however, these subjects were eligible to receive a 90 mg subcutaneous injection of ustekinumab upon entry into trial CD-3. Of these subjects, 102/219 (47%) achieved clinical response eight weeks later and were followed for the duration of the trial.

14.5 Ulcerative Colitis

Ustekinumab was evaluated in two randomized, double-blind, placebo-controlled clinical trials [UC-1 and UC-2 (NCT02407236)] in adult subjects with moderately to severely active ulcerative colitis who had an inadequate response to or failed to tolerate a biologic (i.e., TNF blocker and/or vedolizumab), corticosteroids, and/or 6-MP or AZA therapy. The 8-week intravenous induction trial (UC-1) was followed by the 44-week subcutaneous randomized withdrawal maintenance trial (UC-2) for a total of 52 weeks of therapy.

Disease assessment was based on the Mayo score, which ranged from 0 to 12 and has four subscores that were each scored from 0 (normal) to 3 (most severe): stool frequency, rectal bleeding, findings on centrally-reviewed endoscopy, and physician global assessment. Moderately to severely active ulcerative colitis was defined at baseline (Week 0) as Mayo score of 6 to 12, including a Mayo endoscopy subscore ≥2. An endoscopy score of 2 was defined by marked erythema, absent vascular pattern, friability, erosions; and a score of 3 was defined by spontaneous bleeding, ulceration. At baseline, subjects had a median Mayo score of 9, with 84% of subjects having moderate disease (Mayo score 6–10) and 15% having severe disease (Mayo score 11–12).

Subjects in these trials may have received other concomitant therapies including aminosalicylates, immunomodulatory agents (AZA, 6-MP, or MTX), and oral corticosteroids (prednisone).

Trial UC-1

In UC-1, 961 subjects were randomized at Week 0 to a single intravenous administration of ustekinumab of approximately 6 mg/kg, 130 mg (a lower dose than recommended), or placebo. Subjects enrolled in UC-1 had to have failed therapy with corticosteroids, immunomodulators or at least one biologic. A total of 51% had failed at least one biologic and 17% had failed both a TNF blocker and an integrin receptor blocker. Of the total population, 46% had failed corticosteroids or immunomodulators but were biologic-naïve and an additional 3% had previously received but had not failed a biologic. At induction baseline and throughout the trial, approximately 52% subjects were receiving oral corticosteroids, 28% subjects were receiving immunomodulators (AZA, 6-MP, or MTX) and 69% subjects were receiving aminosalicylates.

The primary endpoint was clinical remission at Week 8. Clinical remission with a definition of: Mayo stool frequency subscore of 0 or 1, Mayo rectal bleeding subscore of 0 (no rectal bleeding), and Mayo endoscopy subscore of 0 or 1 (Mayo endoscopy subscore of 0 defined as normal or inactive disease and Mayo subscore of 1 defined as presence of erythema, decreased vascular pattern and no friability) is provided in Table 15.

The secondary endpoints were clinical response, endoscopic improvement, and histologic-endoscopic mucosal improvement. Clinical response with a definition of (≥ 2 points and ≥ 30% decrease in modified Mayo score, defined as 3-component Mayo score without the Physician's Global Assessment, with either a decrease from baseline in the rectal bleeding subscore ≥1 or a rectal bleeding subscore of 0 or 1), endoscopic improvement with a definition of Mayo endoscopy subscore of 0 or 1, and histologic-endoscopic mucosal improvement with a definition of combined endoscopic improvement and histologic improvement of the colon tissue [neutrophil infiltration in <5% of crypts, no crypt destruction, and no erosions, ulcerations, or granulation tissue]) are provided in Table 15.

In UC-1, a significantly greater proportion of subjects treated with ustekinumab (at the recommended dose of approximately 6 mg/kg dose) were in clinical remission and response and achieved endoscopic improvement and histologic-endoscopic mucosal improvement compared to placebo (see Table 15).

Table 15: Proportion of Subjects Meeting Efficacy Endpoints at Week 8 in UC-1

Endpoint | Placebo; N = 319 |  | Ustekinumab†; N = 322 |  | Treatment difference and; 97.5% CI a
Endpoint | N | % | N | % | Treatment difference and; 97.5% CI a
Clinical Remission* | 22 | 7% | 62 | 19% | 12%; (7%, 18%) b
Bio-naïve⸸ | 14/151 | 9% | 36/147 | 24%
Prior biologic failure | 7/161 | 4% | 24/166 | 14%
Endoscopic Improvement§ | 40 | 13% | 80 | 25% | 12%; (6%, 19%) b
Bio-naïve⸸ | 28/151 | 19% | 43/147 | 29%
Prior biologic failure | 11/161 | 7% | 34/166 | 20%
Clinical Response† | 99 | 31% | 186 | 58% | 27% (18%, 35%) b
Bio-naïve⸸ | 55/151 | 36% | 94/147 | 64%
Prior biologic failure | 42/161 | 26% | 86/166 | 52%
Histologic-Endoscopic Mucosal Improvement‡ | 26 | 8% | 54 | 17% | 9%; (3%, 14%) b
Bio-naïve⸸ | 19/151 | 13% | 30/147 | 20%
Prior biologic failure | 6/161 | 4% | 21/166 | 13%

† Infusion dose of ustekinumab using the weight-based dosage regimen specified in Table 4.

⸸ An additional 7 subjects on placebo and 9 subjects on ustekinumab (6 mg/kg) had been exposed to, but had not failed, biologics.

* Clinical remission was defined as Mayo stool frequency subscore of 0 or 1, Mayo rectal bleeding subscore of 0, and Mayo endoscopy subscore of 0 or 1 (modified so that 1 does not include friability).

§ Endoscopic improvement was defined as Mayo endoscopy subscore of 0 or 1 (modified so that 1 does not include friability).

† Clinical response was defined as a decrease from baseline in the modified Mayo score by ≥30% and ≥2 points, with either a decrease from baseline in the rectal bleeding subscore ≥1 or a rectal bleeding subscore of 0 or 1.

‡ Histologic-endoscopic mucosal improvement was defined as combined endoscopic improvement (Mayo endoscopy subscore of 0 or 1) and histologic improvement of the colon tissue (neutrophil infiltration in <5% of crypts, no crypt destruction, and no erosions, ulcerations, or granulation tissue).

a Adjusted treatment difference (97.5% CI)

b p < 0.001

The relationship of histologic-endoscopic mucosal improvement, as defined in UC-1, at Week 8 to disease progression and long-term outcomes was not evaluated during UC-1.

Rectal Bleeding and Stool Frequency Subscores

Decreases in rectal bleeding and stool frequency subscores were observed as early as Week 2 in ustekinumab-treated subjects.

Trial UC-2

The maintenance trial (UC-2) evaluated 523 subjects who achieved clinical response 8 weeks following the intravenous administration of either induction dose of ustekinumab in UC-1. These subjects were randomized to receive a subcutaneous maintenance regimen of either 90 mg ustekinumab every 8 weeks, or every 12 weeks (a lower dose than recommended), or placebo for 44 weeks.

The primary endpoint was the proportion of subjects in clinical remission at Week 44. The secondary endpoints included the proportion of subjects maintaining clinical response at Week 44, the proportion of subjects with endoscopic improvement at Week 44, the proportion of subjects with corticosteroid-free clinical remission at Week 44, and the proportion of subjects maintaining clinical remission at Week 44 among subjects who achieved clinical remission 8 weeks after induction.

Results of the primary and secondary endpoints at Week 44 in subjects treated with ustekinumab at the recommended dosage (90 mg every 8 weeks) compared to the placebo are shown in Table 16.

Table 16: Efficacy Endpoints of Maintenance at Week 44 in UC-2 (52 Weeks from Initiation of the Induction Dose)

Endpoint | Placebo*; N = 175† |  | 90 mg Ustekinumab; every 8 weeks; N = 176 |  | Treatment difference and 95% CI
Endpoint | N | % | N | % | Treatment difference and 95% CI
Clinical Remission** | 46 | 26% | 79 | 45% | 19%; (9%, 28%) a
Bio-naïve⸸ | 30/84 | 36% | 39/79 | 49%
Prior biologic failure | 16/88 | 18% | 37/91 | 41%
Maintenance of Clinical Response at Week 44† | 84 | 48% | 130 | 74% | 26%; (16%, 36%) a
Bio-naïve⸸ | 49/84 | 58% | 62/79 | 78%
Prior biologic failure | 35/88 | 40% | 64/91 | 70%
Endoscopic Improvement§ | 47 | 27% | 83 | 47% | 20%; (11%, 30%) a
Bio-naïve⸸ | 29/84 | 35% | 42/79 | 53%
Prior biologic failure | 18/88 | 20% | 38/91 | 42%
Corticosteroid-free Clinical Remission‡ | 45 | 26% | 76 | 43% | 17%; (8%, 27%) a
Bio-naïve⸸ | 30/84 | 36% | 38/79 | 48%
Prior biologic failure | 15/88 | 17% | 35/91 | 38%
Maintenance of Clinical Remission at Week 44 in subjects who achieved clinical remission 8 weeks after induction | 18/50 | 36% | 27/41 | 66% | 31%; (12%, 50%) b
Bio-naïve⸸ | 12/27 | 44% | 14/20 | 70%
Prior biologic failure | 6/23 | 26% | 12/18 | 67%

⸸ An additional 3 subjects on placebo and 6 subjects on ustekinumab had been exposed to, but had not failed, biologics.

* The placebo group consisted of subjects who were in response to ustekinumab and were randomized to receive placebo at the start of maintenance therapy.

** Clinical remission was defined as Mayo stool frequency subscore of 0 or 1, Mayo rectal bleeding subscore of 0, and Mayo endoscopy subscore of 0 or 1 (modified so that 1 does not include friability).

† Clinical response was defined as a decrease from baseline in the modified Mayo score by ≥30% and ≥2 points, with either a decrease from baseline in the rectal bleeding subscore ≥1 or a rectal bleeding subscore of 0 or 1.

§ Endoscopic improvement was defined as Mayo endoscopy subscore of 0 or 1 (modified so that 1 does not include friability).

‡ Corticosteroid-free clinical remission was defined as subjects in clinical remission and not receiving corticosteroids at Week 44.

a p =<0.001

Other Endpoints

Week 16 Responders to Ustekinumab Induction

Subjects who were not in clinical response 8 weeks after induction with ustekinumab in UC-1 were not included in the primary efficacy analyses for trial UC-2; however, these subjects were eligible to receive a 90 mg subcutaneous injection of ustekinumab at Week 8. Of these subjects, 55/101 (54%) achieved clinical response eight weeks later (Week 16) and received ustekinumab 90 mg subcutaneously every 8 weeks during the UC-2 trial. At Week 44, there were 97/157 (62%) subjects who maintained clinical response and there were 51/157 (32%) who achieved clinical remission.

Histologic-Endoscopic Mucosal Improvement at Week 44

The proportion of subjects achieving histologic-endoscopic mucosal improvement during maintenance treatment in UC-2 was 75/172 (44%) among subjects on ustekinumab and 40/172 (23%) in subjects on placebo at Week 44. The relationship of histologic-endoscopic mucosal improvement, as defined in UC-2, at Week 44 to progression of disease or long-term outcomes was not evaluated in UC-2.

Endoscopic Normalization

Normalization of endoscopic appearance of the mucosa was defined as a Mayo endoscopic subscore of 0. At Week 8 in UC-1, endoscopic normalization was achieved in 25/322 (8%) of subjects treated with ustekinumab and 12/319 (4%) of subjects in the placebo group. At Week 44 of UC-2, endoscopic normalization was achieved in 51/176 (29%) of subjects treated with ustekinumab and in 32/175 (18%) of subjects in placebo group.

15 REFERENCES

^1 Surveillance, Epidemiology, and End Results (SEER) Program (www.seer.cancer.gov) SEER*Stat Database: Incidence - SEER 6.6.2 Regs Research Data, Nov 2009 Sub (1973–2007) - Linked To County Attributes - Total U.S., 1969–2007 Counties, National Cancer Institute, DCCPS, Surveillance Research Program, Surveillance Systems Branch, released April 2010, based on the November 2009 submission.

16 HOW SUPPLIED/STORAGE AND HANDLING

How Supplied

YESINTEK (ustekinumab-kfce) injection is a sterile, preservative-free, clear and colorless to pale yellow solution. It is supplied as individually packaged, single-dose prefilled syringes or single-dose vials.

For Subcutaneous Use

Prefilled Syringes

- 45 mg/0.5 mL (NDC 83257-023-41)
- 90 mg/mL (NDC 83257-025-41)

Each prefilled syringe is equipped with a 29 gauge fixed ½ inch needle, a needle safety guard, and a needle cover.

Single-dose Vial

- 45 mg/0.5 mL (NDC 83257-024-11)

For Intravenous Infusion

Single-dose Vial

- 130 mg/26 mL (5 mg/mL) (NDC 83257-026-11)

Storage and Stability

Store YESINTEK vials and prefilled syringes refrigerated between 2°C to 8°C (36°F to 46°F). Store YESINTEK vials upright. Keep the product in the original carton to protect from light until the time of use. Do not freeze. Do not shake.

If needed, individual prefilled syringes may be stored at room temperature up to 30°C (86°F) for a maximum single period of up to 30 days in the original carton to protect from light. Record the date when the prefilled syringe is first removed from the refrigerator on the carton in the space provided. Once a syringe has been stored at room temperature, do not return to the refrigerator. Discard the syringe if not used within 30 days at room temperature storage. Do not use YESINTEK after the expiration date on the carton or on the prefilled syringe.

17 PATIENT COUNSELING INFORMATION

Advise the patient and/or caregiver to read the FDA-approved patient labeling (Medication Guide and Instructions for Use).

Infections

Inform patients that YESINTEK may lower the ability of their immune system to fight infections and to contact their healthcare provider immediately if they develop any signs or symptoms of infection [see Warnings and Precautions (5.1)].

Malignancies

Inform patients of the risk of developing malignancies while receiving YESINTEK [see Warnings and Precautions (5.4)].

Serious Hypersensitivity and Reactions

- Inform patients that serious hypersensitivity reactions have been reported with intravenous and subcutaneous administration of ustekinumab products. Instruct patients to discontinue YESINTEK and seek immediate medical attention if they experience any signs or symptoms of hypersensitivity reactions [see Warnings and Precautions (5.5)].

Posterior Reversible Encephalopathy Syndrome (PRES)

Inform patients to immediately contact their healthcare provider if they experience signs and symptoms of PRES (which may include headache, seizures, confusion, or visual disturbances) [see Warnings and Precautions (5.6)].

Immunizations

Inform patients that YESINTEK can interfere with the usual response to immunizations and that they should avoid live vaccines [see Warnings and Precautions (5.7)].

Administration

Instruct patients to follow sharps disposal recommendations, as described in the Instructions for Use.

Manufactured by:

Biocon Biologics Inc.

245 Main St, 2nd Floor

Cambridge, MA 02142 U.S.A.

U.S. License No. 2324

Product of India

© 2026 Biocon Biologics Inc.

Revised: 01/2026

MEDICATION GUIDE

YESINTEKTM (Yes-in-tek)

(ustekinumab-kfce)

injection, for subcutaneous or intravenous use

What is the most important information I should know about YESINTEK?

YESINTEK is a medicine that affects your immune system. YESINTEK can increase your risk of having serious side effects, including:

- Serious infections. YESINTEK may lower the ability of your immune system to fight infections and may increase your risk of infections. Some people have serious infections during treatment with ustekinumab products, including tuberculosis (TB), and infections caused by bacteria, fungi, or viruses. Some people have to be hospitalized for treatment of their infection.
  - Your healthcare provider should check you for TB before starting YESINTEK.
  - If your healthcare provider feels that you are at risk for TB, you may be treated with medicine for TB before you begin treatment with YESINTEK and during treatment with YESINTEK.
  - Your healthcare provider should watch you closely for signs and symptoms of TB while you are being treated with YESINTEK.

You should not start YESINTEK if you have any kind of infection unless your healthcare provider says it is okay.

Before starting YESINTEK, tell your healthcare provider if you:

- think you have an infection or have symptoms of an infection such as:
  - fever, sweat, or chills
  - weight loss
  - muscle aches
  - warm, red, or painful skin or sores on your body
  - cough
  - diarrhea or stomach pain
  - shortness of breath
  - burning when you urinate or urinate more often than normal
  - blood in phlegm
  - feel very tired

- are being treated for an infection or have any open cuts.
- get a lot of infections or have infections that keep coming back.
- have TB or have been in close contact with someone with TB.

After starting YESINTEK, call your healthcare provider right away if you have any symptoms of an infection (see above). These may be signs of infections such as chest infections, or skin infections or shingles that could have serious complications. YESINTEK can make you more likely to get infections or make an infection that you have worse.

- People who have a genetic problem where the body does not make any of the proteins interleukin 12 (IL-12) and interleukin 23 (IL-23) are at a higher risk for certain serious infections. These infections can spread throughout the body and cause death. People who take YESINTEK may also be more likely to get these infections.
- Cancers. YESINTEK may decrease the activity of your immune system and increase your risk for certain types of cancers. Tell your healthcare provider if you have ever had any type of cancer. Some people who are receiving ustekinumab products and have risk factors for skin cancer have developed certain types of skin cancers. During your treatment with YESINTEK, tell your healthcare provider if you develop any new skin growths.

What is YESINTEK?

YESINTEK is a prescription medicine used to treat:

- adults and children 6 years of age and older with moderate to severe plaque psoriasis who may benefit from taking injections or pills (systemic therapy) or phototherapy (treatment using ultraviolet light alone or with pills).
- adults and children 6 years of age and older with active psoriatic arthritis.
- adults with moderately to severely active Crohn’s disease.
- adults with moderately to severely active ulcerative colitis.

It is not known if YESINTEK is safe and effective in children with Crohn’s disease or ulcerative colitis or in children less than 6 years of age with plaque psoriasis or psoriatic arthritis.

Who should not use YESINTEK?

Do not use YESINTEK if you are allergic to ustekinumab products or any of the ingredients in YESINTEK. See the end of this Medication Guide for a complete list of ingredients in YESINTEK.

Before you use or receive YESINTEK, tell your healthcare provider about all of your medical conditions, including if you:

- have any of the conditions or symptoms listed in the section “What is the most important information I should know about YESINTEK?”
- ever had an allergic reaction to ustekinumab products. Ask your healthcare provider if you are not sure.
- have recently received or are scheduled to receive an immunization (vaccine). People who are being treated with YESINTEK should avoid receiving live vaccines. Tell your healthcare provider if anyone in your house needs a live vaccine. The viruses used in some types of live vaccines can spread to people with a weakened immune system and can cause serious problems. You should avoid receiving the BCG vaccine during the one year before receiving YESINTEK or one year after you stop receiving YESINTEK.
- have any new or changing lesions within psoriasis areas or on normal skin.
- are receiving or have received allergy shots, especially for serious allergic reactions. Allergy shots may not work as well for you during treatment with YESINTEK. YESINTEK may also increase your risk of having an allergic reaction to an allergy shot.
- receive or have received phototherapy for your psoriasis.
- are pregnant or plan to become pregnant. It is not known if YESINTEK can harm your unborn baby. You and your healthcare provider should decide if you will receive YESINTEK.
- are breastfeeding or plan to breastfeed. YESINTEK can pass into your breast milk.
- Talk to your healthcare provider about the best way to feed your baby if you receive YESINTEK.

Tell your healthcare provider about all the medicines you take, including prescription and over-the-counter medicines, vitamins, and herbal supplements.

Know the medicines you take. Keep a list of them to show your healthcare provider and pharmacist when you get a new medicine.

How should I use YESINTEK?

- Use YESINTEK exactly as the healthcare provider tells you to. The healthcare provider will determine the right dose of YESINTEK, the amount for each injection, and how often it should be given. Be sure to keep all scheduled follow up appointments.
- Adults with Crohn’s disease and ulcerative colitis will receive the first dose of YESINTEK through a vein in the arm (intravenous infusion) in a healthcare facility by a healthcare provider. It takes at least 1 hour to receive the full dose of medicine. YESINTEK will then be received as an injection under the skin (subcutaneous injection) 8 weeks after the first dose of YESINTEK, as described below.
- Adults and children 6 years of age and older with plaque psoriasis or psoriatic arthritis will receive YESINTEK as an injection under the skin as described below.

- Injecting YESINTEK under the skin
  - YESINTEK is intended for use under the guidance and supervision of a healthcare provider.
  - In children, it is recommended that YESINTEK be administered by a healthcare provider. If a healthcare provider decides that you or a caregiver may give the injections of YESINTEK at home, you or caregiver should receive training on the right way to prepare and inject YESINTEK.
  - Do not try to inject YESINTEK until you have been shown how to inject YESINTEK by a healthcare provider.
  - YESINTEK can be injected under the skin in the upper arms, buttocks, upper legs (thighs) or stomach area (abdomen).
  - Do not give an injection in an area of the skin that is tender, bruised, red or hard.
  - Use a different injection site each time you use YESINTEK.

- If you inject too much YESINTEK, call the healthcare provider or Poison Help line at 1-800-222-1222, or go to the nearest emergency room right away.

Read the detailed Instructions for Use at the end of this Medication Guide for instructions about how to prepare and inject a dose of YESINTEK, and how to properly throw away (dispose of) used needles, syringes, and vials. The syringe, needle, and vial must never be re-used. After the stopper is punctured, YESINTEK can become contaminated by harmful bacteria which could cause an infection if re-used. Therefore, throw away any unused portion of YESINTEK.

What should I avoid while using YESINTEK?

You should avoid receiving a live vaccine during treatment with YESINTEK. See “Before you use or receive YESINTEK, tell your healthcare provider about all of your medical conditions, including if you:”

What are the possible side effects of YESINTEK?

YESINTEK may cause serious side effects, including:

- See “What is the most important information I should know about YESINTEK?”
- Serious allergic reactions. Serious allergic reactions including death can occur with YESINTEK. Stop using YESINTEK and get medical help right away if you get any of the following symptoms of a serious allergic reaction:
  - feeling faint
  - trouble breathing
  - swelling of your face, eyelids, tongue, or throat
  - skin rash
  - chest discomfort

- Posterior Reversible Encephalopathy Syndrome (PRES). PRES is a rare condition that affects the brain and can cause death. Tell your healthcare provider right away if you get any symptoms of PRES during treatment with YESINTEK, including:

o headache o confusion

o seizures o vision problems

- Lung inflammation. Cases of lung inflammation have happened in some people who receive ustekinumab products and may be serious. These lung problems may need to be treated in a hospital. Tell your healthcare provider right away if you develop shortness of breath or a cough that doesn’t go away during treatment with YESINTEK.

The most common side effects of YESINTEK include:

- nasal congestion, sore throat, and runny nose • redness at the injection site
- upper respiratory infections • vaginal yeast infections
- fever • urinary tract infections
- headache • sinus infection
- tiredness • bronchitis
- itching • diarrhea
- nausea and vomiting • stomach pain
- influenza • joint pain

These are not all of the possible side effects of YESINTEK. Call your doctor for medical advice about side effects. You may report side effects to FDA at 1-800-FDA-1088.

You may also report side effects to Biocon Biologics at 1-833-986-1468.

How should I store YESINTEK?

- Store YESINTEK vials and prefilled syringes in a refrigerator between 36°F to 46°F (2°C to 8°C).
- Store YESINTEK vials standing up straight (upright).
- Store YESINTEK in the original carton to protect it from light until time to use it.
- Do not freeze YESINTEK.
- Do not shake YESINTEK.
- If needed, individual YESINTEK prefilled syringes may also be stored at room temperature up to 86ºF (30°C) for a maximum single period of up to 30 days in the original carton to protect from light.
- Record the date when the prefilled syringe is first removed from the refrigerator on the carton in the space provided.
- After a prefilled syringe has been stored at room temperature, do not return it to the refrigerator.
- Throw away (discard) the prefilled syringe if it is not used within 30 days at room temperature storage.
- Do not use YESINTEK after the expiration date on the carton or on the prefilled syringe.

Keep YESINTEK and all medicines out of the reach of children.

General information about the safe and effective use of YESINTEK.

Medicines are sometimes prescribed for purposes other than those listed in a Medication Guide. Do not use YESINTEK for a condition for which it was not prescribed. Do not give YESINTEK to other people, even if they have the same symptoms that you have. It may harm them. You can ask your pharmacist or healthcare provider for information about YESINTEK that was written for health professionals

What are the ingredients in YESINTEK?

Active ingredient: ustekinumab-kfce

Inactive ingredients: Single-dose prefilled syringe and single-dose vial for subcutaneous use contain histidine, L-histidine monohydrochloride monohydrate, Polysorbate 80, and sucrose. Hydrochloric acid and sodium hydroxide added to adjust the pH. Single-dose vial for intravenous infusion contains edetate disodium, histidine, L-histidine hydrochloride monohydrate, methionine, Polysorbate 80, and sucrose. Hydrochloric acid and sodium hydroxide added to adjust the pH.

Manufactured by :

Biocon Biologics Inc.

245 Main St, 2nd Floor

Cambridge, MA 02142 U.S.A.

U.S. License No. 2324

Product of India

© 2026 Biocon Biologics Inc.

For more information go to www.yesintek.com or call 1-833-986-1468.

This Medication Guide has been approved by the U.S. Food and Drug Administration.

Revised: 01/2026

INSTRUCTIONS FOR USE

YESINTEKTM (Yes-in-tek)

(ustekinumab-kfce)

injection, for subcutaneous use.

This Instructions for Use contains information on how to inject YESINTEK using a prefilled syringe.

Read this Instructions for Use before you start using YESINTEK. A healthcare provider should show you how to prepare and give an injection of YESINTEK the right way.

If you cannot give the injection:

- ask a healthcare provider to help you, or
- ask someone who has been trained by a healthcare provider to give the injections.

Do not try to inject YESINTEK until you have been shown how to inject YESINTEK by a healthcare provider.

Important information You Need to Know Before Injecting YESINTEK:

- For subcutaneous use only (inject directly under the skin).
- Before you start, check the carton to make sure that it is the right dose. You will have either 45 mg or 90 mg as prescribed by the healthcare provider.
  - If the dose is 45 mg, you will receive one 45 mg prefilled syringe.
  - If the dose is 90 mg, you will receive either one 90 mg prefilled syringe or two 45 mg prefilled syringes. If you receive two 45 mg prefilled syringes for a 90 mg dose, you will need to give two injections, one right after the other.

- Check the expiration date on the prefilled syringe and carton. If the expiration date has passed or if the prefilled syringe has been kept at room temperature up to 86°F (30°C) for longer than a maximum single period of 30 days or if the prefilled syringe has been stored above 86°F (30°C), do not use it. If the expiration date has passed or if the prefilled syringe has been stored above 86°F (30°C), or at room temperature for longer than 30 days, call the healthcare provider or pharmacist, or call Biocon Biologics at 1-833-986-1468 for help.

- Make sure the syringe is not damaged.

- Check the prefilled syringe for any particles or discoloration. The liquid in the prefilled syringe should look clear and colorless to pale yellow.
- Do not use if it is frozen, discolored, cloudy or has large particles. Get a new prefilled syringe.
- Do not shake the prefilled syringe at any time. Shaking the prefilled syringe may damage the YESINTEK medicine. If the prefilled syringe has been shaken, do not use it. Get a new prefilled syringe.
- To reduce the risk of accidental needle sticks, each prefilled syringe has a needle guard that is automatically activated to cover the needle after you have given the injection. Do not pull back on the plunger at any time. Do not attempt to remove the needle safety guard from the prefilled syringe.

Storing YESINTEK prefilled syringes

- Store YESINTEK prefilled syringes in the refrigerator between 36ºF to 46ºF (2ºC to 8ºC).

- Store YESINTEK prefilled syringes in the original carton to protect from light.
- Do not freeze YESINTEK prefilled syringes.
- If needed, YESINTEK prefilled syringe may be stored at room temperature up to 86°F (30°C) for a maximum single period of up to 30 days in the original carton to protect from light.
- Record the date when the prefilled syringe is removed from the refrigerator on the carton in the space provided.
- After a prefilled syringe has been stored at room temperature, do not return it to the refrigerator.
- Throw away (discard) the prefilled syringe if it is not used within 30 days at room temperature storage

Keep YESINTEK and all medicines out of the reach of children.

Gather the supplies you will need to prepare and to give the injection. (See Figure A)

You will need:

- your prescribed dose of YESINTEK (See Figure B)
- antiseptic wipes
- cotton balls or gauze pads
- adhesive bandage
- FDA-cleared sharps disposal container. See "Step 4: Disposing of the syringes."

Step 1: Preparing the injection.

- Choose a well-lit, clean, flat work surface.
- Wash your hands well with soap and warm water. Remove prefilled syringe tray from carton
- Open the tray by peeling away the cover. Hold the prefilled syringe by the Needle safety guard (as shown in Figure C) to remove the prefilled syringe from the tray.

For safety reasons:

- Do not touch or grasp the plunger
- Do not grasp the gray needle cover

- Hold the prefilled syringe with the covered needle pointing upward.

Step 2: Preparing the injection site

- Choose an injection site around the stomach area (abdomen), buttocks, upper legs (thighs). If a caregiver is giving the injection, the outer area of the upper arms may also be used. (See Figure D)
- Use a different injection site for each injection. Do not give an injection in an area of the skin that is tender, bruised, red or hard.
- Clean the skin with an antiseptic wipe where you plan to give the injection.
- Do not touch this area again before giving the injection. Let the skin dry before injecting.
- Do not fan or blow on the clean area.

*Areas in blue are recommended injection sites.

Step 3: Injecting YESINTEK

- Remove the needle cover when you are ready to inject YESINTEK.
- Do not touch the plunger or plunger head while removing the needle cover.
- Hold the body of the prefilled syringe with one hand and pull the needle cover straight off. (See Figure E)
- Put the needle cover in the trash.
- You may also see a drop of liquid at the end of the needle. This is normal.
- Do not touch the needle or let it touch anything.
- Do not use the prefilled syringe if it is dropped without the needle cover in place.

- Hold the body of the prefilled syringe in one hand between the thumb and index fingers. (See Figure F)

- Do not pull back on the plunger at any time.
- Use the other hand to gently pinch the cleaned area of skin. Hold firmly.
- Use a quick, dart-like motion to insert the needle into the pinched skin at about a 45-degree angle. (See Figure G)

- Inject all of the liquid by using your thumb to push in the plunger until the plunger head is completely between the needle guard wings. (See Figure H)

- When the plunger is pushed as far as it will go, keep pressure on the plunger head. Take the needle out of the skin and then let go of the skin.
- Slowly take your thumb off the plunger head. This will let the empty syringe move up until the entire needle is covered by the needle guard. (See Figure I)

- When the needle is pulled out of the skin, there may be a little bleeding at the injection site. This is normal. You can press a cotton ball or gauze pad to the injection site if needed. Do not rub the injection site. You may cover the injection site with a small adhesive bandage, if necessary.

If the dose is 90 mg, you will receive either one 90 mg prefilled syringe or two 45 mg prefilled syringes. If you receive two 45 mg prefilled syringes for a 90 mg dose, you will need to give a second injection right after the first. Repeat Steps 1 to 3 for the second injection using a new syringe. Choose a different site for the second injection.

Step 4: Disposing of the syringes.

- Put the syringe in an FDA-cleared sharps disposal container right away after use. Do not throw away (dispose of) syringes in your household trash.
- If you do not have an FDA-cleared sharps disposal container, you may use a household container that is:
  - made of heavy-duty plastic,
  - can be closed with a tight-fitting, puncture-resistant lid, without sharps being able to come out,
  - upright and stable during use,
  - leak-resistant,
  - and properly labeled to warn of hazardous waste inside the container.

- When your sharps disposal container is almost full, you will need to follow your community guidelines for the right way to dispose of your sharps disposal container. There may be local or state laws about how to throw away syringes and needles. For more information about safe sharps disposal, and for specific information about sharps disposal in the state that you live in, go to the FDA's website at: http://www.fda.gov/safesharpsdisposal.
- Do not dispose of your sharps disposal container in your household trash unless your community guidelines permit this. Do not recycle your sharps disposal container.
- If you have any questions, talk to your healthcare provider or pharmacist.

Manufactured by:

Biocon Biologics Inc.

245 Main St, 2nd Floor

Cambridge, MA 02142 U.S.A.

U.S. License No. 2324

Product of India

© 2026 Biocon Biologics Inc.

This Instructions for Use has been approved by the U.S. Food and Drug Administration.

Revised: 01/2026

INSTRUCTIONS FOR USE

YESINTEKTM (Yes-in-tek)

(ustekinumab-kfce)

injection, for subcutaneous use

This Instructions for Use contains information on how to inject YESINTEK using a vial.

Read this Instructions for Use before you start using YESINTEK. A healthcare provider should show you how to prepare, measure the dose, and give an injection of YESINTEK the right way.

If you cannot give the injection:

- ask a healthcare provider to help you, or
- ask someone who has been trained by a healthcare provider to give the injections.

Do not try to inject YESINTEK until you have been shown how to inject YESINTEK by a healthcare provider.

Important information You Need to Know Before Injecting YESINTEK:

- Before you start, check the carton to make sure that it is the right dose. You will have either 45 mg or 90 mg as prescribed by the healthcare provider.
  - If the dose is 45 mg or less, you will receive one 45 mg vial.
  - If the dose is 90 mg, you will receive two 45 mg vials and you will need to give two injections, one right after the other.

- Check the expiration date on the vial and carton. If the expiration date has passed, do not use it. If the expiration date has passed, call the healthcare provider or pharmacist, or call Biocon Biologics at 1-833-986-1468 for help.
- Check the vial for any particles or discoloration. The liquid in the vial should look clear and colorless to pale yellow solution.
- Do not use if it is frozen, discolored, cloudy or has large particles. Get a new vial.
- Do not shake the vial at any time. Shaking the vial may damage the YESINTEK medicine. If the vial has been shaken, do not use it. Get a new vial.
- Do not use a YESINTEK vial more than one time, even if there is medicine left in the vial. After the rubber stopper is punctured, YESINTEK can become contaminated by harmful bacteria which could cause an infection if re-used. Therefore, throw away any unused YESINTEK after you give the injection.
- Safely throw away (dispose of) YESINTEK vials, needles, and syringes after use. See “Step 6: Disposing of needles, syringes, and vials.”
- Do not re-use syringes or needles.
- To avoid needle-stick injuries, do not recap needles.

Storing YESINTEK vials

- Store YESINTEK vials in a refrigerator between 36ºF to 46ºF (2ºC to 8ºC).
- Store YESINTEK vials standing up straight (upright).
- Store YESINTEK vials in the original carton to protect from light until the time of use.
- Do not freeze YESINTEK vials.

Keep YESINTEK and all medicines out of the reach of children.

Gather the supplies you will need to prepare YESINTEK and to give the injection. (See Figure A)

You will need:

- a syringe with the needle attached, you will need a prescription from a healthcare provider to get syringes with the needles attached from a pharmacy.
- antiseptic wipes
- cotton balls or gauze pads
- adhesive bandage

- your prescribed dose of YESINTEK

- FDA-cleared sharps disposal container. See “Step 6: Disposing of needles, syringes and vials.”

Figure A

Step 1: Preparing the injection

- Choose a well-lit, clean, flat work surface.
- Wash your hands well with soap and warm water.

Step 2: Preparing your injection site

- Choose an injection site around the stomach area (abdomen), buttocks, and upper legs (thighs).
- If a caregiver is giving the injection, the outer area of the upper arms may also be used. (See Figure B)
- Use a different injection site for each injection. Do not give an injection in an area of the skin that is tender, bruised, red or hard.
- Clean the skin with an antiseptic wipe where you plan to give the injection.
- Do not touch this area again before giving the injection. Let the skin dry before injecting.
- Do not fan or blow on the clean area.

Figure B

*Areas in gray are recommended injection sites

Step 3: Preparing the vial

- Remove the cap from the top of the vial. Throw away the cap but do not remove the rubber stopper. (See Figure C)

Figure C

- Clean the rubber stopper with an antiseptic wipe. (See Figure D)

Figure D

- Do not touch the rubber stopper after you clean it.
- Put the vial on a flat surface.

Step 4: Preparing the syringe

- Pick up the syringe with the needle attached.
- Remove the cap that covers the needle. (See Figure E)
- Throw the needle cap away. Do not touch the needle or allow the needle to touch anything.

Figure E

- Carefully pull back on the plunger to the line that matches the dose prescribed by the healthcare provider.
- Hold the vial between your thumb and index (pointer) finger.
- Use your other hand to push the syringe needle through the center of the rubber stopper. (See Figure F)

Figure F

- Push down on the plunger until all of the air has gone from the syringe into the vial.
- Turn the vial and the syringe upside down. (See Figure G)
- Hold the YESINTEK vial with one hand.
- It is important that the needle is always in the liquid in order to prevent air bubbles forming in the syringe.
- Pull back on the syringe plunger with your other hand.
- Fill the syringe until the black tip of the plunger lines up with the mark that matches the prescribed dose.

Figure G

- Do not remove the needle from the vial. Hold the syringe with the needle pointing up to see if it has any air bubbles inside.
- If there are air bubbles, gently tap the side of the syringe until the air bubbles rise to the top. (See Figure H)
- Slowly press the plunger up until all of the air bubbles are out of the syringe (but none of the liquid is out).
- Remove the syringe from the vial. Do not lay the syringe down or allow the needle to touch anything.

Figure H

Step 5: Injecting YESINTEK

- Hold the barrel of the syringe in one hand, between the thumb and index fingers.
- Do not pull back on the plunger at any time.
- Use the other hand to gently pinch the cleaned area of skin. Hold firmly.
- Use a quick, dart-like motion to insert the needle into the pinched skin at about a 45-degree angle. (See Figure I)

Figure I

- Push the plunger with your thumb as far as it will go to inject all of the liquid. Push it slowly and evenly, keeping the skin gently pinched.
- When the syringe is empty, pull the needle out of the skin and then let go of the skin. (See Figure J)

Figure J

- When the needle is pulled out of the skin, there may be a little bleeding at the injection site. This is normal. You can press a cotton ball or gauze pad to the injection site if needed. Do not rub the injection site. You may cover the injection site with a small adhesive bandage, if necessary.

If the dose is 90 mg, you will receive two 45 mg vials and you will need to give a second injection right after the first. Repeat Steps 1 to 5 using a new syringe. Choose a different site for the second injection.

Step 6: Disposing of needles, syringes, and vials.

- Do not re-use a syringe or needle.
- To avoid needle-stick injuries, do not recap a needle.
- Put the needles and syringes in an FDA-cleared sharps disposal container right away after use. Do not throw away (dispose of) needles and syringes in your household trash.
- If you do not have an FDA-cleared sharps disposal container, you may use a household container that is:
  - made of heavy-duty plastic,
  - can be closed with a tight-fitting, puncture-resistant lid, without sharps being able to come out,
  - upright and stable during use,
  - leak-resistant,
  - and properly labeled to warn of hazardous waste inside the container.

- When your sharps disposal container is almost full, you will need to follow your community guidelines for the right way to dispose of your sharps disposal container. There may be local or state laws about how to throw away syringes and needles. For more information about safe sharps disposal, and for specific information about sharps disposal in the state that you live in, go to the FDA’s website at: http://www.fda.gov/safesharpsdisposal.

- Do not dispose of your sharps disposal container in your household trash unless your community guidelines permit this. Do not recycle your sharps disposal container.
- Throw away the vial into the container where you put the syringes and needles.
- If you have any questions, talk to your healthcare provider or pharmacist.

Manufactured by:

Biocon Biologics Inc.

245 Main St, 2nd Floor

Cambridge, MA 02142 U.S.A.

U.S. License No. 2324

Product of India

© 2026 Biocon Biologics Inc.

This Instructions for Use has been approved by the U.S. Food and Drug Administration.

Revised: 01/2026

PRINCIPAL DISPLAY PANEL - 45 mg/0.5 mL Syringe Carton

NDC 83257-023-41

YesintekTM
(ustekinumab-kfce)
Injection

45 mg/0.5 mL

For Subcutaneous use

Contains one 45 mg/0.5 mL syringe

Single-dose prefilled syringe

Discard unused portion

Each 0.5 mL prefilled syringe delivers 45 mg ustekinumab-kfce, histidine, L-histidine monohydrochloride monohydrate (0.5 mg), Polysorbate 80 (0.02 mg), and sucrose (38 mg).

Hydrochloric acid and sodium hydroxide are used to adjust pH to 5.7- 6.3 during manufacturing.

Dosage: See Prescribing Information.

Rx only

ATTENTION: Dispense the enclosed medication guide to each patient.

Storage: Refrigerate at 36º F to 46º F (2º C to 8º C) in the original carton to protect from light. Do not freeze. Do not shake.

Keep out of reach of Children.

Prefilled syringe can be stored at room temperature up to 86°F (30°C) for up to 30 days in the original carton to protect from light. Once stored at room temperature, do not place back in the refrigerator.

Write the date removed from the refrigerator ____/____/______.

Discard if not used within 30 days at room temperature.

Do not use YesintekTM injection after the expiration date on the carton or on the prefilled syringe.

No preservative.

Manufactured by:

Biocon Biologics Inc.

245 Main St, 2nd Floor Cambridge, MA 02142 U.S.A.

U.S. License No. 2324

Product of India

Mfg. Lic. No.: KTK/29/8253/2020

PRINCIPAL DISPLAY PANEL - 90 mg/mL Syringe Carton

NDC 83257-025-41

YesintekTM
(ustekinumab-kfce)
Injection

90 mg/mL

For subcutaneous use

Contains one 90 mg/mL syringe

Single-dose prefilled syringe

Discard unused portion

Dosage: See Prescribing Information.

Rx only

ATTENTION: Dispense the enclosed medication guide to each patient.

Each 1 mL prefilled syringe delivers 90 mg ustekinumab-kfce, histidine, L-histidine monohydrochloride monohydrate (1 mg), Polysorbate 80 (0.04 mg), and sucrose (76 mg).

Hydrochloric acid and sodium hydroxide are used to adjust pH to 5.7- 6.3 during manufacturing.

Storage: Refrigerate at 36º F to 46º F (2º C to 8º C) in the original carton to protect from light. Do not freeze. Do not shake.

Keep out of reach of Children.

Prefilled syringe can be stored at room temperature up to 86°F (30°C) for up to 30 days in the original carton to protect from light. Once stored at room temperature, do not place back in the refrigerator.

Write the date removed from the refrigerator ____/____/______.

Discard if not used within 30 days at room temperature.

Do not use YesintekTM injection after the expiration date on the carton or on the prefilled syringe.

No preservative.

Manufactured by:

Biocon Biologics Inc.

245 Main St, 2nd Floor Cambridge, MA 02142 U.S.A.

U.S. License No. 2324

Product of India

Mfg. Lic. No.: KTK/29/8253/2020

PRINCIPAL DISPLAY PANEL - 130 mg/26 mL Vial Carton

NDC 83257-026-11

YesintekTM
(ustekinumab-kfce)
Injection

130 mg/26 mL
(5 mg/mL)

For Intravenous Infusion Only
Must be diluted
Single-dose vial
Discard unused portion

ATTENTION: Dispense the enclosed Medication Guide to each patient

Rx only

Dosage: See Prescribing Information

Each 26 mL vial delivers 130 mg ustekinumab-kfce, edetate disodium (0.47 mg), histidine (20 mg), L-histidine hydrochloride monohydrate (27 mg), methionine (10.4 mg), Polysorbate 80 (10.4 mg), and sucrose (2210 mg).

No preservative.

Hydrochloric acid and sodium hydroxide are used to adjust pH to 5.7- 6.3 during manufacturing.

Storage: Refrigerate at 36º F to 46º F (2º C to 8º C) in the original carton to protect from light. Do not freeze. Do not shake. Keep out of the reach of children

Mfg. Lic. No.: KTK/29/8253/2020

Manufactured by:

Biocon Biologics Inc.

245 Main St, 2nd Floor Cambridge,

MA 02142 U.S.A.

U.S. License No. 2324

Product of India

© 2024 Biocon Biologics Inc.

PRINCIPAL DISPLAY PANEL - 45 mg/0.5 mL Vial Carton

NDC 83257-024-11

YesintekTM
(ustekinumab-kfce)
Injection

45 mg/0.5 mL Vial

For subcutaneous use
Single-dose vial
Discard unused portion

ATTENTION: Dispense the enclosed medication guide to each patient.

Rx only

For subcutaneous use

Dosage: See Prescribing Information

Each 0.5 mL vial delivers 45 mg ustekinumab-kfce, histidine, L-histidine monohydrochloride monohydrate (0.5 mg), Polysorbate 80 (0.02 mg), and sucrose (38 mg).

Hydrochloric acid and sodium hydroxide are used to adjust pH to 5.7- 6.3 during manufacturing.

No preservative

Storage: Refrigerate at 36º F to 46º F (2º C to 8º C) in the original carton to protect from light. Do not freeze. Do not shake. Keep out of the reach of children

Mfg. Lic. No.: KTK/29/8253/2020

Manufactured by:

Biocon Biologics Inc.

245 Main St, 2nd Floor

Cambridge, MA 02142 U.S.A.

U.S. License No. 2324

Product of India

© 2024 Biocon Biologics Inc.